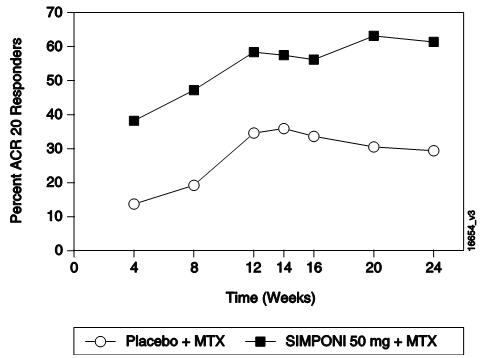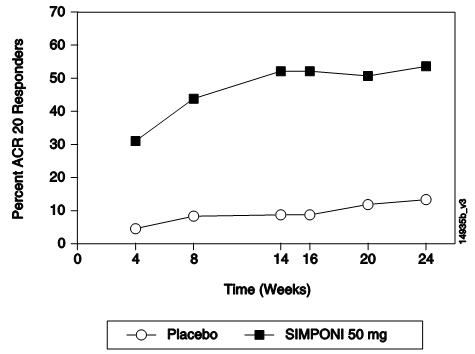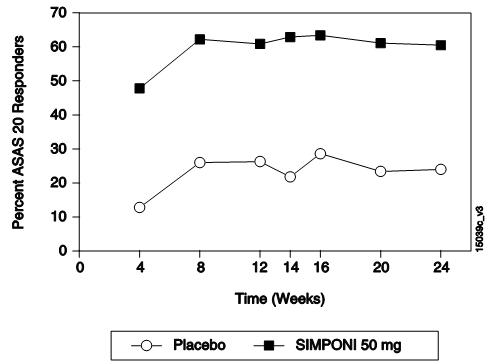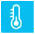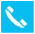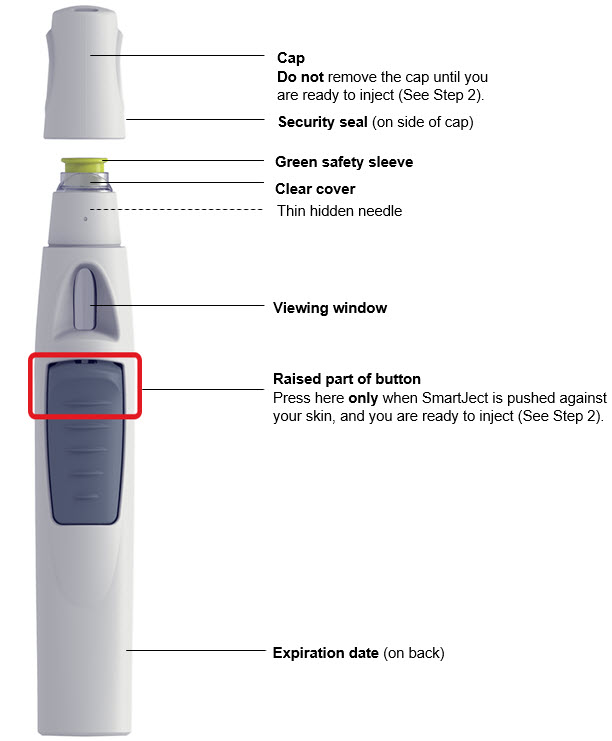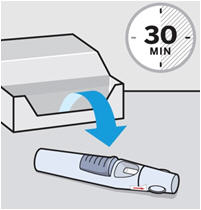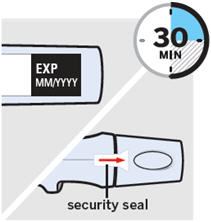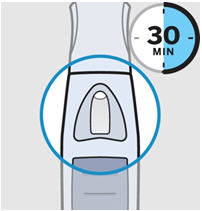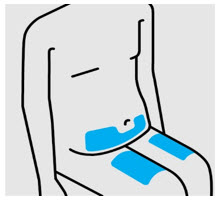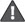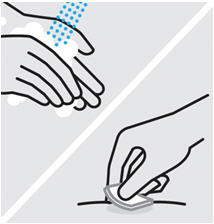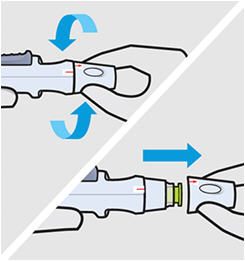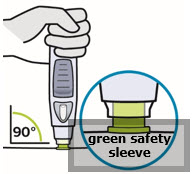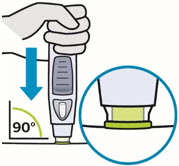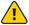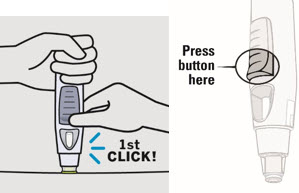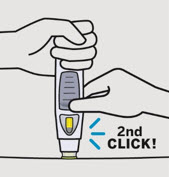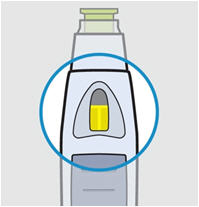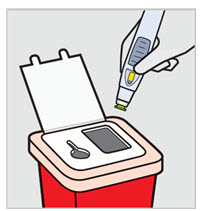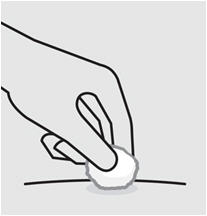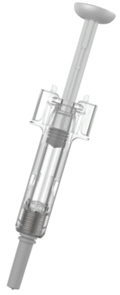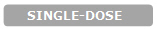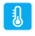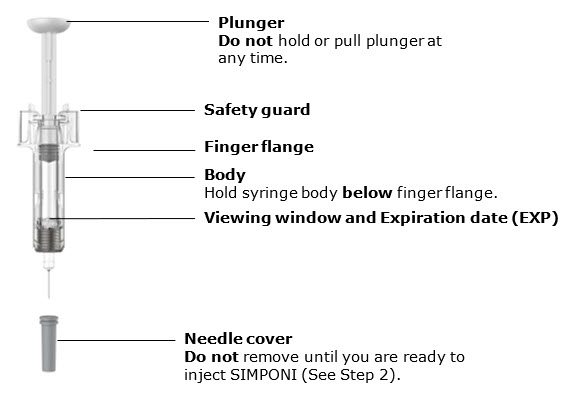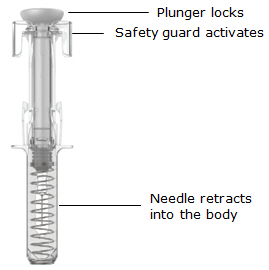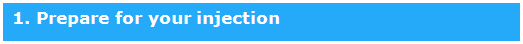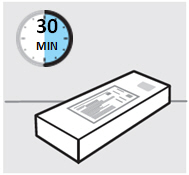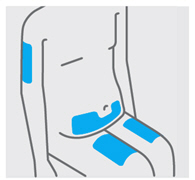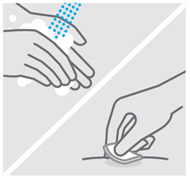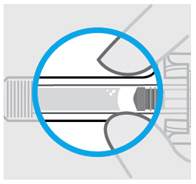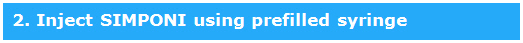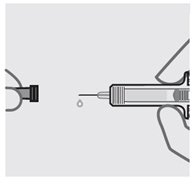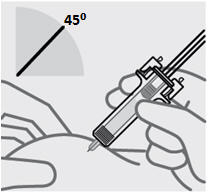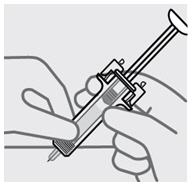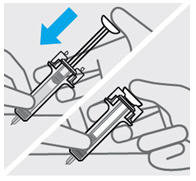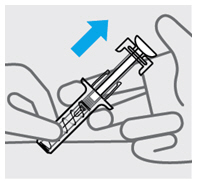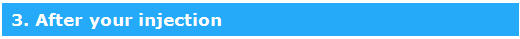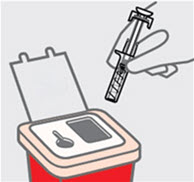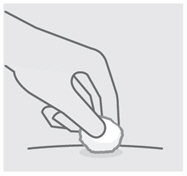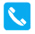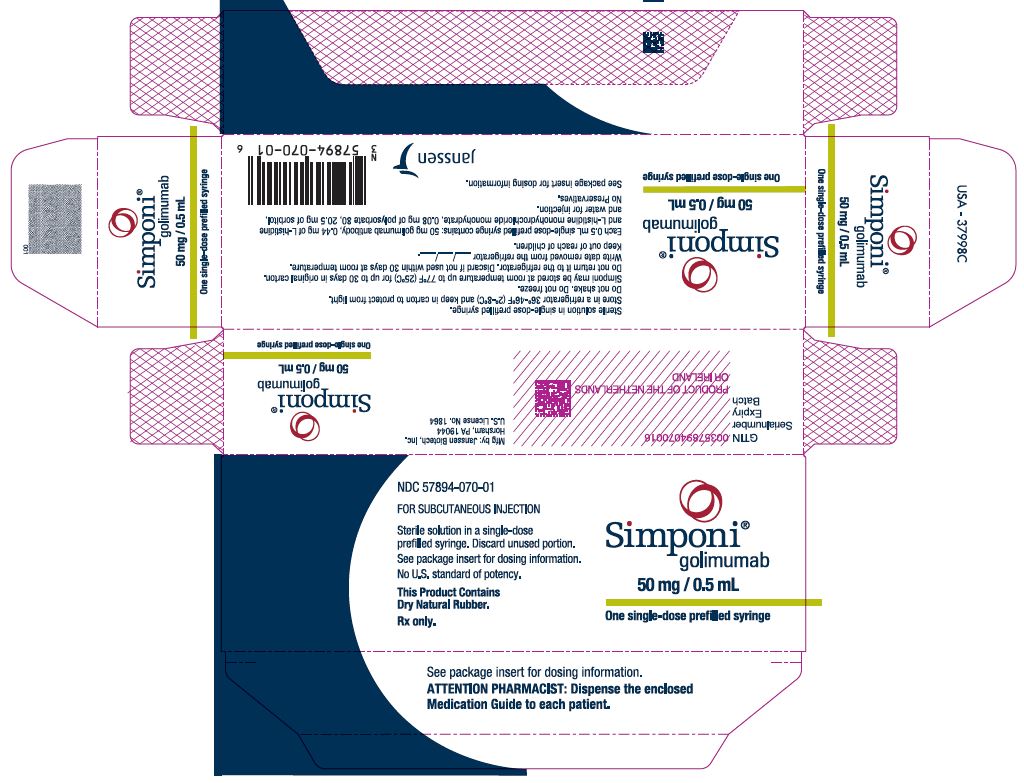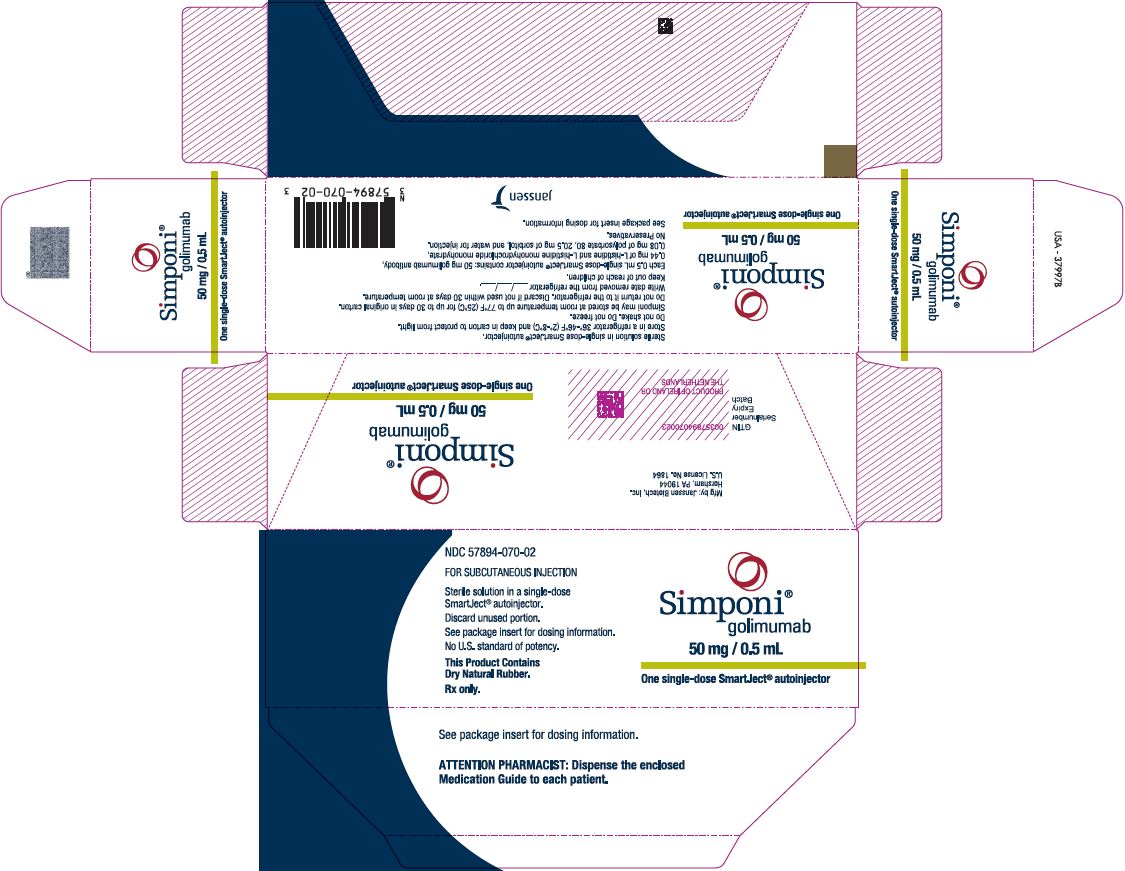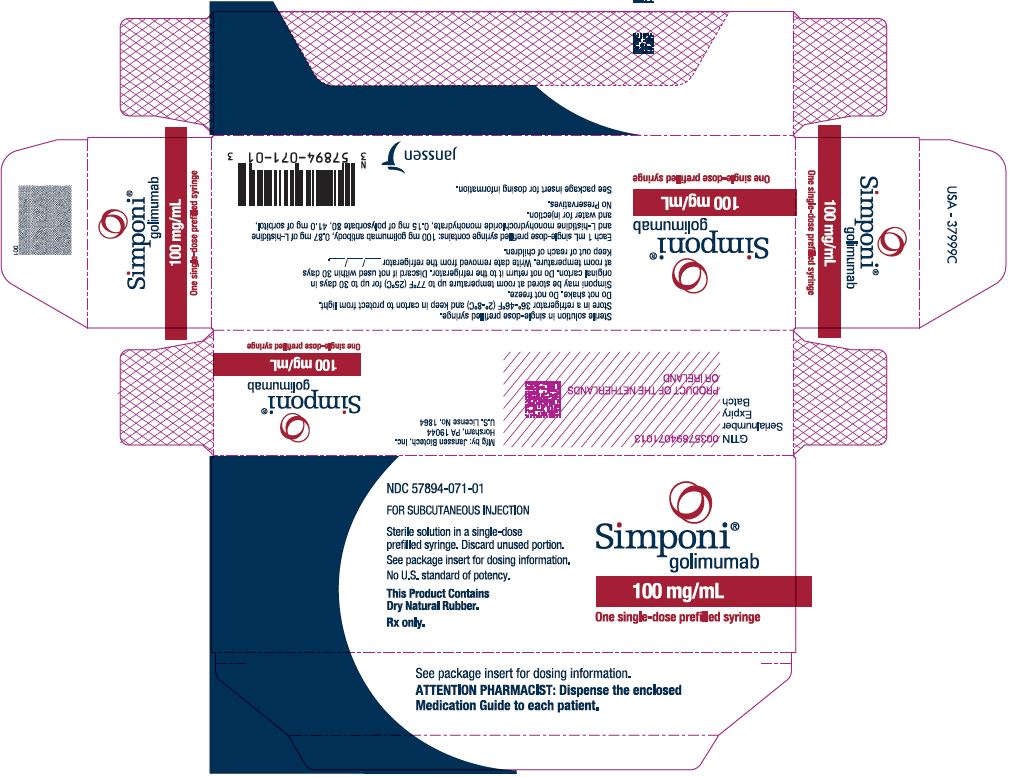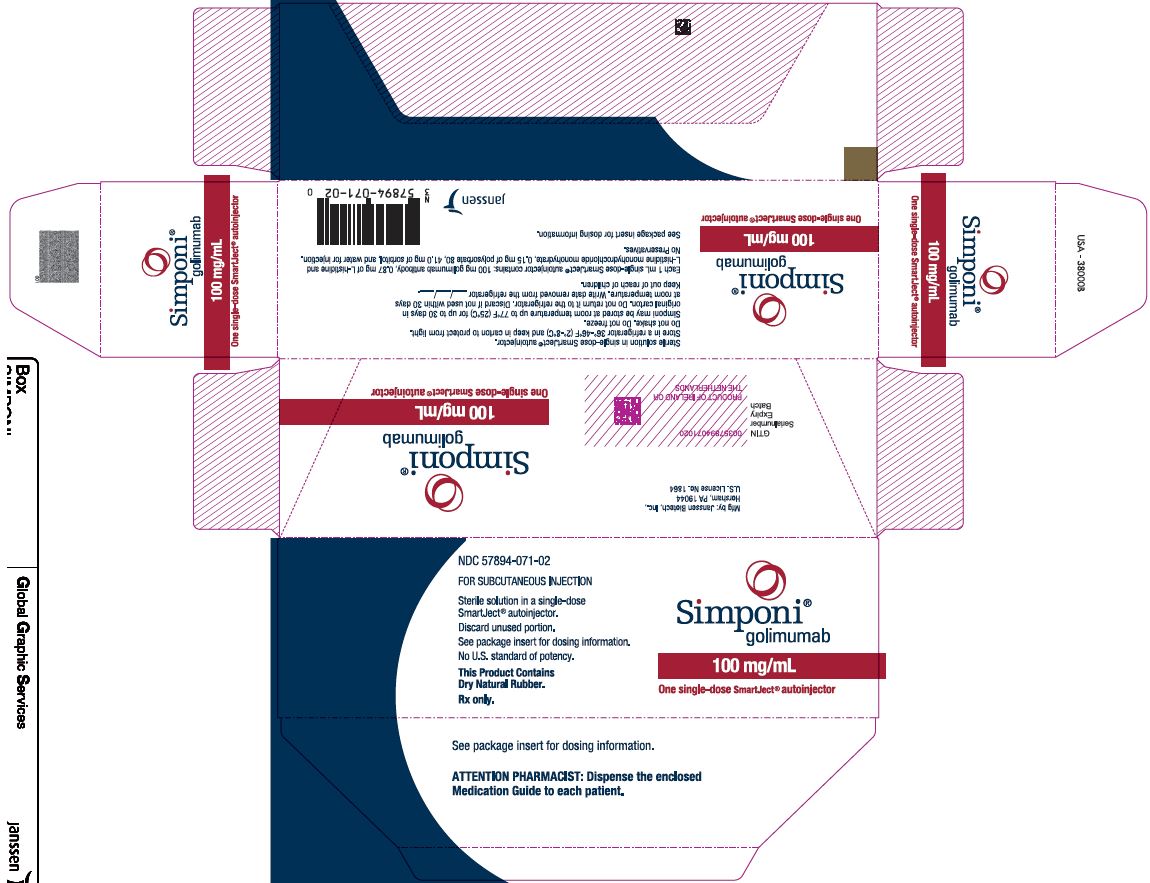 DRUG LABEL: Simponi
NDC: 57894-070 | Form: INJECTION, SOLUTION
Manufacturer: Janssen Biotech, Inc.
Category: prescription | Type: HUMAN PRESCRIPTION DRUG LABEL
Date: 20251029

ACTIVE INGREDIENTS: GOLIMUMAB 50 mg/0.5 mL
INACTIVE INGREDIENTS: HISTIDINE 0.44 mg/0.5 mL; HISTIDINE HYDROCHLORIDE MONOHYDRATE; SORBITOL 20.5 mg/0.5 mL; POLYSORBATE 80 0.08 mg/0.5 mL; WATER

HIGHLIGHTS OF PRESCRIBING INFORMATION

These highlights do not include all the information needed to use SIMPONI safely and effectively. See full prescribing information for SIMPONI.
SIMPONI®(golimumab) injection, for subcutaneous use
Initial U.S. Approval: 2009

WARNING: SERIOUS INFECTIONS AND MALIGNANCY

See full prescribing information for complete boxed warning.

- Serious infections leading to hospitalization or death including tuberculosis (TB), bacterial sepsis, invasive fungal (such as histoplasmosis), and other opportunistic infections have occurred in patients receiving SIMPONI (5.1)
- Discontinue SIMPONI if a patient develops a serious infection or sepsis (5.1)
- Perform test for latent TB; if positive, start treatment for TB prior to starting SIMPONI (5.1)
- Monitor all patients for active TB during treatment, even if initial latent TB test is negative (5.1)
- Lymphoma and other malignancies, some fatal, have been reported in children and adolescent patients treated with TNF blockers, of which SIMPONI is a member (5.2)

RECENT MAJOR CHANGES

Indications and Usage (1.4) | 10/2025
Dosage and Administration (2.1, 2.3, 2.4) | 10/2025
Warnings and Precautions (5.11) | 10/2025

1 INDICATIONS AND USAGE

SIMPONI is a tumor necrosis factor (TNF) blocker indicated for the treatment of:

- adult patients with moderately to severely active rheumatoid arthritis (RA) in combination with methotrexate (1.1)
- adult patients with active psoriatic arthritis (PsA) alone, or in combination with methotrexate (1.2)
- adult patients with active ankylosing spondylitis (AS) (1.3)
- adult and pediatric patients weighing at least 15 kg with moderately to severely active ulcerative colitis (UC) (1.4)

2 DOSAGE AND ADMINISTRATION

- RA, PsA, and AS: 50 mg administered by subcutaneous injection once a month (2.2)
- UC: The recommended dosage and administration by subcutaneous injection in adults and pediatric patients weighing at least 15 kg is shown in the table (2.3)

Recommended Dosage
Weight for Patients with UC | Week 0 | Week 2 | Week 6 and every 4 weeks thereafter
Adults and pediatric patients 40 kg and greater [For pediatric patients weighing 15 kg or greater, administer the appropriate dose using the prefilled syringe (50 mg/0.5 mL or 100 mg/mL).] | 200 mg | 100 mg | 100 mg
Pediatric patients at least 15 kg to less than 40 kg | 100 mg | 50 mg | 50 mg

3 DOSAGE FORMS AND STRENGTHS

Injection (3):

- 50 mg/0.5 mL in a single-dose prefilled syringe or single-dose prefilled SmartJect®autoinjector
- 100 mg/mL in a single-dose prefilled syringe or single-dose prefilled SmartJect®autoinjector

4 CONTRAINDICATIONS

None (4)

5 WARNINGS AND PRECAUTIONS

- Serious Infections: Do not start SIMPONI during an active infection. If an infection develops, monitor carefully, and stop SIMPONI if infection becomes serious (5.1)
- Invasive Fungal Infections: For patients who develop a systemic illness on SIMPONI, consider empiric antifungal therapy for those who reside in or travel to regions where mycoses are endemic (5.1)
- Malignancies: Incidence of lymphoma was greater than in the general U.S. population. Cases of other malignancies have been observed among patients receiving TNF blockers (5.2)
- Congestive Heart Failure: Worsening, or new onset, may occur. Stop SIMPONI if new or worsening symptoms occur (5.3)
- Demyelinating Disorders: Exacerbation or new onset may occur (5.4)
- Hepatitis B Reactivation: Monitor HBV carriers during and several months after therapy. If reactivation occurs, stop SIMPONI and begin antiviral therapy (5.5)
- Lupus-like Syndrome: Discontinue SIMPONI if symptoms develop (5.6)
- Hypersensitivity Reactions: Serious systemic hypersensitivity reactions including anaphylaxis may occur (5.12)

6 ADVERSE REACTIONS

Most common adverse reactions in adults (incidence > 5%) are upper respiratory tract infection, nasopharyngitis, injection site reactions (6.1)

To report SUSPECTED ADVERSE REACTIONS, contact Janssen Biotech, Inc. at 1-800-JANSSEN (1-800-526-7736) or FDA at 1-800-FDA-1088 or www.fda.gov/medwatch.

7 DRUG INTERACTIONS

- Abatacept: Increased risk of serious infection (5.1, 5.7, 7.2)
- Anakinra: Increased risk of serious infection (5.1, 5.8, 7.2)
- Live vaccines/therapeutic infectious agents: Avoid use with SIMPONI (5.11, 7.3).

FULL PRESCRIBING INFORMATION

WARNING: SERIOUS INFECTIONS AND MALIGNANCY

SERIOUS INFECTIONS

Patients treated with SIMPONI are at increased risk for developing serious infections that may lead to hospitalization or death [see Warnings and Precautions (5.1)] . Most patients who developed these infections were taking concomitant immunosuppressants such as methotrexate or corticosteroids.

Discontinue SIMPONI if a patient develops a serious infection.

Reported infections with TNF blockers, of which SIMPONI is a member, include:

- Active tuberculosis, including reactivation of latent tuberculosis. Patients with tuberculosis have frequently presented with disseminated or extrapulmonary disease. Test patients for latent tuberculosis before SIMPONI use and during therapy. Initiate treatment for latent TB prior to SIMPONI use.
- Invasive fungal infections including histoplasmosis, coccidioidomycosis, candidiasis, aspergillosis, blastomycosis, and pneumocystosis. Patients with histoplasmosis or other invasive fungal infections may present with disseminated, rather than localized, disease. Antigen and antibody testing for histoplasmosis may be negative in some patients with active infection. Consider empiric antifungal therapy in patients at risk for invasive fungal infections who develop severe systemic illness.
- Bacterial, viral, and other infections due to opportunistic pathogens, including Legionella and Listeria.

Consider the risks and benefits of treatment with SIMPONI prior to initiating therapy in patients with chronic or recurrent infection.

Monitor patients closely for the development of signs and symptoms of infection during and after treatment with SIMPONI, including the possible development of tuberculosis in patients who tested negative for latent tuberculosis infection prior to initiating therapy [see Warnings and Precautions (5.1)] .

MALIGNANCY

Lymphoma and other malignancies, some fatal, have been reported in children and adolescent patients treated with TNF blockers, of which SIMPONI is a member [see Warnings and Precautions (5.2)] .

1 INDICATIONS AND USAGE

1.1 Rheumatoid Arthritis

SIMPONI, in combination with methotrexate, is indicated for the treatment of adult patients with moderately to severely active rheumatoid arthritis.

1.2 Psoriatic Arthritis

SIMPONI, alone or in combination with methotrexate, is indicated for the treatment of adult patients with active psoriatic arthritis.

1.3 Ankylosing Spondylitis

SIMPONI is indicated for the treatment of adult patients with active ankylosing spondylitis.

1.4 Ulcerative Colitis

SIMPONI is indicated for the treatment of adults and pediatric patients weighing at least 15 kg with moderately to severely active ulcerative colitis.

2 DOSAGE AND ADMINISTRATION

2.1 Recommended Evaluations and Immunizations Before Initiating SIMPONI

Prior to initiating treatment with SIMPONI:

- Evaluate patients for active tuberculosis and test for latent infection [see Warnings and Precautions (5.1)].
- Test patients for hepatitis B viral infection.
- If possible, complete all age-appropriate vaccinations according to current immunization guidelines [see Warnings and Precautions (5.11)].

2.2 Recommended Dosage for Rheumatoid Arthritis, Psoriatic Arthritis, Ankylosing Spondylitis

The recommended SIMPONI dosage in adults is 50 mg administered by subcutaneous injection once a month.

For patients with rheumatoid arthritis (RA), SIMPONI should be given in combination with methotrexate and for patients with psoriatic arthritis (PsA) or ankylosing spondylitis (AS), SIMPONI may be given with or without methotrexate or other nonbiologic Disease-Modifying Antirheumatic Drugs (DMARDs). For patients with RA, PsA, or AS, corticosteroids, non-biologic DMARDs, and/or NSAIDs may be continued during treatment with SIMPONI.

2.3 Recommended Dosage for Moderately to Severely Active Ulcerative Colitis in Adults and Pediatric Patients Weighing at least 15 kg

The recommended dosage is shown in Table 1.

Table 1: Recommended Subcutaneous Dosage for Adults and Pediatric Patients Weighing at least 15 kg with Moderately to Severely Active Ulcerative Colitis
Weight for Patients with UC | Recommended Dosage of SIMPONI
Weight for Patients with UC | Week 0 | Week 2 | Week 6 and every 4 weeks thereafter
Adults and pediatric patients 40 kg and greater [For pediatric patients weighing 15 kg or greater, administer the appropriate dose using the prefilled syringe (50 mg/0.5 mL or 100 mg/mL).] | 200 mg | 100 mg | 100 mg
Pediatric patients at least 15 kg to less than 40 kg | 100 mg | 50 mg | 50 mg

2.4 Preparation and Administration Instructions

SIMPONI is intended for use under the guidance and supervision of a healthcare provider after proper training in subcutaneous injection technique. Patients may self-inject with SIMPONI if a physician determines that it is appropriate. Instruct patients to follow the directions provided in the Instructions for Use.

SIMPONI Prefilled Syringe

- Adult and pediatric patients 12 years of age and older may self-inject with SIMPONI prefilled syringe.

SIMPONI SmartJect® Autoinjector

- Adult patients may self-inject with SIMPONI SmartJect® autoinjector.
- Use of the SmartJect® autoinjector for pediatric self-administration has not been evaluated.

• To ensure proper use, allow the prefilled syringe or autoinjector to sit at room temperature outside the carton for at least 30 minutes prior to subcutaneous injection. Do not warm SIMPONI in any other way.

• Prior to administration, visually inspect the solution for particles and discoloration through the viewing window. SIMPONI is clear to slightly opalescent and colorless to light yellow. Do not use SIMPONI, if the solution is discolored, or cloudy, or if foreign particles are present.

• Do not use any leftover product remaining in the prefilled syringe or prefilled autoinjector.

• Instruct patients sensitive to latex not to handle the needle cover on the prefilled syringe or the needle cover of the prefilled syringe within the autoinjector cap because it contains dry natural rubber (a derivative of latex).

• At the time of dosing, if multiple injections are required, administer the injections at different sites on the body.

• Rotate injection sites and never give injections into areas where the skin is tender, bruised, red, or hard.

• If a dose is missed, administer the dose as soon as possible. Thereafter, resume dosing at the regular scheduled time.

3 DOSAGE FORMS AND STRENGTHS

Injection: 50 mg/0.5 mL and 100 mg/mL clear to slightly opalescent, colorless to light yellow solution in a single-dose prefilled syringe or single-dose SmartJect® autoinjector.

4 CONTRAINDICATIONS

None.

5 WARNINGS AND PRECAUTIONS

5.1 Serious Infections

Patients treated with SIMPONI are at increased risk for developing serious infections involving various organ systems and sites that may lead to hospitalization or death.

Opportunistic infections due to bacterial, mycobacterial, invasive fungal, viral, or parasitic organisms including aspergillosis, blastomycosis, candidiasis, coccidioidomycosis, histoplasmosis, legionellosis, listeriosis, pneumocystosis, and tuberculosis have been reported with TNF blockers. Patients have frequently presented with disseminated rather than localized disease. The concomitant use of a TNF blocker and abatacept or anakinra was associated with a higher risk of serious infections; therefore, the concomitant use of SIMPONI and these biologic products is not recommended [see Warnings and Precautions (5.6, 5.7) and Drug Interactions (7.2)] .

Treatment with SIMPONI should not be initiated in patients with an active infection, including clinically important localized infections. Patients greater than 65 years of age, patients with co-morbid conditions and/or patients taking concomitant immunosuppressants such as corticosteroids or methotrexate may be at greater risk of infection. Consider the risks and benefits of treatment prior to initiating SIMPONI in patients:

- with chronic or recurrent infection;
- who have been exposed to tuberculosis;
- with a history of an opportunistic infection;
- who have resided or traveled in areas of endemic tuberculosis or endemic mycoses, such as histoplasmosis, coccidioidomycosis, or blastomycosis; or
- with underlying conditions that may predispose them to infection.

Monitoring

Closely monitor patients for the development of signs and symptoms of infection during and after treatment with SIMPONI. Discontinue SIMPONI if a patient develops a serious infection, an opportunistic infection, or sepsis. For a patient who develops a new infection during treatment with SIMPONI, perform a prompt and complete diagnostic workup appropriate for an immunocompromised patient, initiate appropriate antimicrobial therapy, and closely monitor them.

Serious Infection in Clinical Trials

In controlled Phase 3 trials through Week 16 in patients with RA, PsA, and AS, serious infections were observed in 1.4% of SIMPONI-treated patients and 1.3% of control-treated patients. In the controlled Phase 3 trials through Week 16 in patients with RA, PsA, and AS, the incidence of serious infections per 100 patient-years of follow-up was 5.7 (95% CI: 3.8, 8.2) for the SIMPONI group and 4.2 (95% CI: 1.8, 8.2) for the placebo group. In the controlled Phase 2/3 trial through Week 6 of SIMPONI induction in UC, the incidence of serious infections in SIMPONI 200/100 mg-treated patients was similar to the incidence of serious infections in placebo-treated patients. Through Week 60, the incidence of serious infections was similar in patients who received SIMPONI induction and 100 mg during maintenance compared with patients who received SIMPONI induction and placebo during the maintenance portion of the UC trial. Serious infections observed in SIMPONI-treated patients included sepsis, pneumonia, cellulitis, abscess, tuberculosis, invasive fungal infections, and hepatitis B infection.

Tuberculosis

Cases of reactivation of tuberculosis or new tuberculosis infections have been observed in patients receiving TNF blockers, including patients who have previously received treatment for latent or active tuberculosis. Evaluate patients for tuberculosis risk factors and test for latent infection prior to initiating SIMPONI and periodically during therapy.

Treatment of latent tuberculosis infection prior to therapy with TNF blockers has been shown to reduce the risk of tuberculosis reactivation during therapy. Prior to initiating SIMPONI, assess if treatment for latent tuberculosis is needed; an induration of 5 mm or greater is a positive tuberculin skin test, even for patients previously vaccinated with Bacille Calmette-Guerin (BCG).

Consider anti-tuberculosis therapy prior to initiation of SIMPONI in patients with a past history of latent or active tuberculosis in whom an adequate course of treatment cannot be confirmed, and for patients with a negative test for latent tuberculosis but having risk factors for tuberculosis infection. Consultation with a physician with expertise in the treatment of tuberculosis is recommended to aid in the decision whether initiating anti-tuberculosis therapy is appropriate for an individual patient.

Cases of active tuberculosis have occurred in patients treated with SIMPONI during and after treatment for latent tuberculosis. Monitor patients for the development of signs and symptoms of tuberculosis including patients who tested negative for latent tuberculosis infection prior to initiating therapy, patients who are on treatment for latent tuberculosis, or patients who were previously treated for tuberculosis infection.

Consider tuberculosis in the differential diagnosis in patients who develop a new infection during SIMPONI treatment, especially in patients who have previously or recently traveled to countries with a high prevalence of tuberculosis, or who have had close contact with a person with active tuberculosis.

In the controlled and uncontrolled portions of the Phase 2 RA and Phase 3 RA, PsA, and AS trials, the incidence of active TB was 0.23 and 0 per 100 patient-years in 2347 SIMPONI-treated patients and 674 placebo-treated patients, respectively. Cases of TB included pulmonary and extrapulmonary TB. The overwhelming majority of the TB cases occurred in countries with a high incidence rate of TB. In the controlled Phase 2/3 trial of SIMPONI induction through Week 6 in UC, no cases of TB were observed in SIMPONI 200/100 mg-treated patients or in placebo-treated patients. Through Week 60, the incidence per 100 patient-years of TB in patients who received SIMPONI induction and 100 mg during the maintenance portion of the UC trial was 0.52 (95% CI: 0.11, 1.53). One case of TB was observed in the placebo maintenance group in a patient who received SIMPONI intravenous (IV) induction.

Invasive Fungal Infections

If patients develop a serious systemic illness and they reside or travel in regions where mycoses are endemic, consider invasive fungal infection in the differential diagnosis. Consider appropriate empiric antifungal therapy, and take into account both the risk for severe fungal infection and the risks of antifungal therapy while a diagnostic workup is being performed. Antigen and antibody testing for histoplasmosis may be negative in some patients with active infection. To aid in the management of such patients, consider consultation with a physician with expertise in the diagnosis and treatment of invasive fungal infections.

5.2 Malignancies

Malignancies, some fatal, have been reported among children, adolescents, and young adults who received treatment with TNF-blocking agents (initiation of therapy ≤ 18 years of age), of which SIMPONI is a member. Approximately half the cases were lymphomas, including Hodgkin's and non-Hodgkin's lymphoma. The other cases represented a variety of malignancies, including rare malignancies that are usually associated with immunosuppression, and malignancies that are not usually observed in children and adolescents. The malignancies occurred after a median of 30 months (range 1 to 84 months) after the first dose of TNF-blocker therapy. Most of the patients were receiving concomitant immunosuppressants. These cases were reported postmarketing and are derived from a variety of sources, including registries and spontaneous postmarketing reports.

The risks and benefits of TNF-blocker treatment, including SIMPONI, should be considered prior to initiating therapy in patients with a known malignancy other than a successfully treated nonmelanoma skin cancer (NMSC) or when considering continuing a TNF-blocker in patients who develop a malignancy.

In the controlled portions of clinical trials of TNF blockers, including SIMPONI, more cases of lymphoma have been observed among patients receiving anti-TNF treatment compared with patients in the control groups. During the controlled portions of the Phase 2 trials in RA, and the Phase 3 trials in RA, PsA and AS, the incidence of lymphoma per 100 patient-years of follow-up was 0.21 (95% CI: 0.03, 0.77) in the combined SIMPONI group compared with an incidence of 0 (95% CI: 0, 0.96) in the placebo group. In the controlled and uncontrolled portions of these clinical trials in 2347 SIMPONI-treated patients with a median follow-up of 1.4 years, the incidence of lymphoma was 3.8-fold higher than expected in the general U.S. population according to the 1964–2004 data from SEER database (adjusted for age, gender, and race). Through Week 60 of the UC trials, there were no cases of lymphoma with SIMPONI. Patients with RA and other chronic inflammatory diseases, particularly patients with highly active disease and/or chronic exposure to immunosuppressant therapies, may be at higher risk (up to several fold) than the general population for the development of lymphoma, even in the absence of TNF-blocking therapy. Cases of acute and chronic leukemia have been reported with TNF-blocker use, including SIMPONI, in rheumatoid arthritis and other indications. Even in the absence of TNF-blocker therapy, patients with rheumatoid arthritis may be at a higher risk (approximately 2-fold) than the general population for the development of leukemia.

Rare postmarketing cases of hepatosplenic T-cell lymphoma (HSTCL) have been reported in patients treated with TNF-blocking agents. This rare type of T-cell lymphoma has a very aggressive disease course and is usually fatal. Nearly all of the reported TNF blocker associated cases have occurred in patients with Crohn's disease or ulcerative colitis. The majority were in adolescent and young adult males. Almost all these patients had received treatment with azathioprine (AZA) or 6-mercaptopurine (6–MP) concomitantly with a TNF blocker at or prior to diagnosis. The potential risk with the combination of AZA or 6-MP and SIMPONI should be carefully considered. A risk for the development for hepatosplenic T-cell lymphoma in patients treated with TNF blockers cannot be excluded.

During the controlled portions of the Phase 2 trial in RA, and the Phase 3 trials in RA, PsA and AS, the incidence of malignancies other than lymphoma per 100 patient-years of follow-up was not elevated in the combined SIMPONI group compared with the placebo group. In the controlled and uncontrolled portions of these trials, the incidence of malignancies, other than lymphoma, in SIMPONI-treated patients was similar to that expected in the general U.S. population according to the 1969–2004 SEER database (adjusted for age, gender, and race). In the 6-week placebo-controlled portions of the SIMPONI Phase 2/3 clinical trials in UC, the incidence of non-lymphoma malignancies (excluding nonmelanoma skin cancer) was similar between the SIMPONI and the placebo group. Through Week 60, the incidence of non-lymphoma malignancies (excluding nonmelanoma skin cancer) was similar to the general U.S. population according to the 1969–2004 SEER database (adjusted for age, gender, and race). Short follow-up periods, such as those of one year or less in the studies above, may not adequately reflect the true incidence of malignancies.

It is not known if SIMPONI treatment influences the risk for developing dysplasia or colon cancer. All patients with ulcerative colitis who are at increased risk for dysplasia or colon carcinoma (for example, patients with long-standing ulcerative colitis or primary sclerosing cholangitis), or who had a prior history of dysplasia or colon carcinoma should be screened for dysplasia at regular intervals before therapy and throughout their disease course. This evaluation should include colonoscopy and biopsies per local recommendations. In patients with newly diagnosed dysplasia treated with SIMPONI, the risks and benefits to the individual patient must be carefully reviewed and consideration should be given to whether therapy should be continued.

Melanoma and Merkel cell carcinoma have been reported in patients treated with TNF-blocking agents, including SIMPONI. Periodic skin examination is recommended for all patients, particularly those with risk factors for skin cancer.

In controlled trials of other TNF blockers in patients at higher risk for malignancies (e.g., patients with chronic obstructive pulmonary disease [COPD], patients with Wegener's granulomatosis treated with concomitant cyclophosphamide) a greater portion of malignancies occurred in the TNF-blocker group compared to the controlled group. In an exploratory 1-year clinical trial evaluating the use of 50 mg, 100 mg, and 200 mg of SIMPONI in 309 patients with severe persistent asthma, 6 patients developed malignancies other than NMSC in the SIMPONI groups compared to none in the control group. Three of the 6 patients were in the 200 mg SIMPONI group.

5.3 Congestive Heart Failure

Cases of worsening congestive heart failure (CHF) and new onset CHF have been reported with TNF blockers, including SIMPONI. Some cases had a fatal outcome. In several exploratory trials of other TNF blockers in the treatment of CHF, there were greater proportions of TNF-blocker-treated patients who had CHF exacerbations requiring hospitalization or increased mortality. SIMPONI has not been studied in patients with a history of CHF and SIMPONI should be used with caution in patients with CHF. If a decision is made to administer SIMPONI to patients with CHF, these patients should be closely monitored during therapy, and SIMPONI should be discontinued if new or worsening symptoms of CHF appear.

5.4 Demyelinating Disorders

Use of TNF blockers, of which SIMPONI is a member, has been associated with rare cases of new onset or exacerbation of central nervous system (CNS) demyelinating disorders, including multiple sclerosis (MS) and peripheral demyelinating disorders, including Guillain-Barré syndrome. Cases of central demyelination, MS, optic neuritis, and peripheral demyelinating polyneuropathy have rarely been reported in patients treated with SIMPONI [see Adverse Reactions (6.1)] . Prescribers should exercise caution in considering the use of TNF blockers, including SIMPONI, in patients with central or peripheral nervous system demyelinating disorders. Discontinuation of SIMPONI should be considered if these disorders develop.

5.5 Hepatitis B Virus Reactivation

The use of TNF blockers including SIMPONI has been associated with reactivation of hepatitis B virus (HBV) in patients who are chronic hepatitis B carriers (i.e., surface antigen positive). In some instances, HBV reactivation occurring in conjunction with TNF blocker therapy has been fatal. The majority of these reports have occurred in patients who received concomitant immunosuppressants.

All patients should be tested for HBV infection before initiating TNF-blocker therapy. For patients who test positive for hepatitis B surface antigen, consultation with a physician with expertise in the treatment of hepatitis B is recommended before initiating TNF-blocker therapy. The risks and benefits of treatment should be considered prior to prescribing TNF blockers, including SIMPONI, to patients who are carriers of HBV. Adequate data are not available on whether antiviral therapy can reduce the risk of HBV reactivation in HBV carriers who are treated with TNF blockers. Patients who are carriers of HBV and require treatment with TNF blockers should be closely monitored for clinical and laboratory signs of active HBV infection throughout therapy and for several months following termination of therapy.

In patients who develop HBV reactivation, TNF blockers should be stopped and antiviral therapy with appropriate supportive treatment should be initiated. The safety of resuming TNF blockers after HBV reactivation has been controlled is not known. Therefore, prescribers should exercise caution when considering resumption of TNF blockers in this situation and monitor patients closely.

5.6 Autoimmunity

Treatment with TNF blockers, including SIMPONI, may result in the formation of antinuclear antibodies (ANA) and, rarely, in the development of a lupus-like syndrome [see Adverse Reactions (6.1)] . If a patient develops symptoms suggestive of a lupus-like syndrome following treatment with SIMPONI, treatment should be discontinued.

5.7 Use with Abatacept

In controlled trials, the concurrent administration of another TNF blocker and abatacept was associated with a greater proportion of serious infections than the use of a TNF blocker alone; and the combination therapy, compared to the use of a TNF blocker alone, has not demonstrated improved clinical benefit in the treatment of RA. Therefore, the combination of TNF blockers, including SIMPONI, and abatacept is not recommended [see Drug Interactions (7.2)] .

5.8 Use with Anakinra

Concurrent administration of anakinra (an interleukin-1 antagonist) and another TNF blocker was associated with a greater portion of serious infections and neutropenia and no additional benefits compared with the TNF-blocker alone. Therefore, the combination of anakinra with TNF blockers, including SIMPONI, is not recommended [see Drug Interactions (7.2)] .

5.9 Switching Between Biological Disease-Modifying Antirheumatic Drugs

Care should be taken when switching from one biological product to another biological product since overlapping biological activity may further increase the risk of infection.

5.10 Hematologic Cytopenias

There have been reports of pancytopenia, leukopenia, neutropenia, agranulocytosis, aplastic anemia, and thrombocytopenia in patients receiving golimumab. Caution should be exercised when using TNF blockers, including SIMPONI, in patients who have or have had significant cytopenias.

5.11 Vaccinations/Therapeutic Infectious Agents

Live Vaccines

Patients treated with SIMPONI may receive vaccinations, except for live vaccines. In patients receiving anti-TNF therapy, limited data are available on the response to live vaccination, or on the secondary transmission of infection by live vaccines. Use of live vaccines could result in clinical infections, including disseminated infections.

If possible, it is recommended that prior to initiating therapy with SIMPONI, pediatric patients be brought up to date with all immunizations in agreement with current immunization guidelines.

Therapeutic Infectious Agents

Other uses of therapeutic infectious agents such as live attenuated bacteria (e.g., BCG bladder instillation for the treatment of cancer) could result in clinical infections, including disseminated infections. It is recommended that therapeutic infectious agents not be given concurrently with SIMPONI.

Non-live Vaccines

In the Phase 3 PsA trial, after pneumococcal vaccination, a similar proportion of SIMPONI-treated and placebo-treated patients were able to mount an adequate immune response of at least a 2-fold increase in antibody titers to pneumococcal polysaccharide vaccine. In both SIMPONI-treated and placebo-treated patients, the proportions of patients with response to pneumococcal vaccine were lower among patients receiving MTX compared with patients not receiving MTX. The data suggest that SIMPONI does not suppress the humoral immune response to the pneumococcal vaccine.

5.12 Hypersensitivity Reactions

In postmarketing experience, serious systemic hypersensitivity reactions (including anaphylactic reaction) have been reported following SIMPONI administration. Some of these reactions occurred after the first administration of SIMPONI. If an anaphylactic or other serious allergic reaction occurs, administration of SIMPONI should be discontinued immediately and appropriate therapy instituted.

6 ADVERSE REACTIONS

The following clinically significant adverse reactions are described elsewhere in the labeling:

- Serious Infections [see Warnings and Precautions (5.1)]
- Malignancies [see Warnings and Precautions (5.2)]
- Congestive Heart Failure [see Warnings and Precautions (5.3)]
- Demyelinating Disorders [see Warnings and Precautions (5.4)]
- Hepatitis B Reactivation [see Warnings and Precautions (5.5)]
- Autoimmunity [see Warnings and Precautions (5.6)]
- Hematologic Cytopenias [see Warnings and Precautions (5.10)]
- Hypersensitivity Reactions [see Warnings and Precautions (5.12)]

6.1 Clinical Trials Experience

Because clinical trials are conducted under widely varying conditions, adverse reaction rates observed in the clinical trials of a drug cannot be directly compared to rates in the clinical trials of another drug and may not reflect the rates observed in clinical practice.

The safety data described below are based on:

- Five pooled, randomized, double-blind, controlled Phase 3 trials in patients with RA, PsA, and AS (Trials RA-1, RA-2, RA-3, PsA, and AS) [see Clinical Studies (14.1, 14.2, and 14.3)] . These 5 trials included 639 control-treated patients and 1659 SIMPONI-treated patients including 1089 with RA, 292 with PsA, and 278 with AS.
- Three pooled, randomized, double-blind, controlled Phase 2/3 in 1233 SIMPONI-treated adult patients with UC (Trials UC-1, UC-2, and UC-3 (NCT03596645)) [see Clinical Studies (14.4)].
- An open-label trial in 69 SIMPONI-treated pediatric patients weighing at least 15 kg with UC (Trial UC-3) (NCT03596645) [see Clinical Studies (14.5)].

The proportion of adult patients who discontinued treatment due to adverse reactions in the controlled Phase 3 trials through Week 16 in RA, PsA and AS was 2% for SIMPONI-treated patients and 3% for placebo-treated patients. The most common adverse reactions leading to discontinuation of SIMPONI in the controlled Phase 3 trials in RA, PsA and AS through Week 16 were sepsis (0.2%), alanine aminotransferase increased (0.2%), and aspartate aminotransferase increased (0.2%). The most common adverse drug reactions leading to discontinuation through Week 60 of the UC trials in adult patients who received SIMPONI induction and 100 mg during maintenance compared with patients who received SIMPONI induction and placebo during maintenance were tuberculosis (0.3% vs. 0.6%) and anemia (0.3% vs. 0%), respectively.

Upper respiratory tract infection and nasopharyngitis were the most common adverse reactions reported in the combined Phase 3 RA, PsA and AS trials in adults through Week 16, occurring in 7% and 6% of SIMPONI-treated patients as compared with 6% and 5% of control-treated patients, respectively.

Infections

In adult controlled Phase 3 trials through Week 16 in RA, PsA, and AS, infections were observed in 28% of SIMPONI-treated patients compared to 25% of control-treated patients. For serious infections, see the Warnings and Precautions section [see Warnings and Precautions (5.1)] . In Trial UC-1, the rates of infections were similar in SIMPONI 200/100 mg-treated patients and placebo-treated patients, or approximately 12%. Through Week 60, the incidence per patient year of infections was similar in patients who received SIMPONI induction and 100 mg during maintenance compared with patients who received SIMPONI induction and placebo during the maintenance period Trial UC-2.

Demyelinating Disorders

In Trial UC-1 of SIMPONI induction through Week 6, no cases of demyelination were observed in SIMPONI 200/100 mg-treated patients or placebo-treated patients. Through Week 60 in Trial UC-2, there were no cases of demyelination in the SIMPONI 100 mg group during maintenance. One case of CNS demyelination was observed in the placebo maintenance group in a patient who received SIMPONI 400/200 mg during induction.

Liver Enzyme Elevations

There have been reports of severe hepatic reactions including acute liver failure in patients receiving TNF blockers. In adult controlled Phase 3 trials of SIMPONI in patients with RA, PsA, and AS through Week 16, ALT elevations ≥ 5 × ULN occurred in 0.2% of control-treated patients and 0.7% of SIMPONI-treated patients and ALT elevations ≥ 3 × ULN occurred in 2% of control-treated patients and 2% of SIMPONI-treated patients. Since many of the patients in the Phase 3 trials for RA, PsA, and AS were also taking medications that cause liver enzyme elevations (e.g., NSAIDs, MTX), the relationship between SIMPONI and liver enzyme elevation is not clear.

In Trials UC-1, UC-2, and UC-3, the incidence of ALT elevations ≥ 5 × ULN was similar in SIMPONI-treated patients and placebo-treated patients, or approximately 1%, with an average duration of follow-up of 46 weeks and 18 weeks, respectively. ALT elevations ≥ 3 × ULN occurred in 2.0% of SIMPONI-treated patients compared with 1.5% of placebo-treated patients with an average duration of follow-up of 46 weeks and 18 weeks, respectively.

Autoimmune Disorders and Autoantibodies

In the adult controlled Phase 3 trials in patients with RA, PsA, and AS through Week 14, there was no association of SIMPONI treatment and the development of newly positive anti-dsDNA antibodies. In Phase 3 trials in RA, PsA, and AS through 1 year of follow-up, 4.0% of SIMPONI-treated patients and 2.6% of control patients were newly antinuclear antibody (ANA)-positive (at titers of 1:160 or greater). The frequency of anti-dsDNA antibodies at 1 year of follow-up was uncommon in patients who were anti-dsDNA negative at baseline. Through Week 60 of the UC trials (Trials UC-1, UC-2, and UC-3), 3.5% of patients who received SIMPONI induction and 100 mg during maintenance were newly ANA-positive (at titers of 1:160 or greater) compared with 3.5% of patients who received SIMPONI induction and placebo during the maintenance period in Trial UC-2. The frequency of anti-dsDNA antibodies at 1 year of follow-up in patients who were anti-dsDNA negative at baseline was 0.5% in patients receiving SIMPONI induction and 100 mg during maintenance compared with 0% in patients who received SIMPONI induction and placebo during maintenance [see Warnings and Precautions (5.6)].

Injection Site Reactions

In adult controlled Phase 3 trials through Week 16 in RA, PsA and AS, 6% of SIMPONI-treated patients had injection site reactions compared with 2% of control-treated patients. The majority of the injection site reactions were mild and the most frequent manifestation was injection site erythema.

In Trial UC-1, 3.4% of SIMPONI-treated patients had injection site reactions compared with 1.5% in control-treated patients. The majority of the injection site reactions were mild and moderate and the most frequent manifestation was injection site erythema.

In adult controlled Phase 2 and 3 trials in RA, PsA, AS, no patients treated with SIMPONI developed anaphylactic reactions.

Other Adverse Reactions

Table 2 summarizes the adverse drug reactions that occurred at a rate of at least 1% in the SIMPONI ± DMARD group and with a higher incidence than in the placebo ± DMARD group during the controlled period of the 5 pooled Phase 3 trials through Week 16 in adult patients with RA, PsA, and AS.

Table 2: Adverse Drug Reactions Reported by ≥ 1% of SIMPONI-Treated Patients and with a Higher Incidence Than Placebo-Treated Patients in the Adult Phase 3 Trials of RA, PsA, and AS through Week 16 [Patients may have taken concomitant MTX, sulfasalazine, hydroxychloroquine, low dose corticosteroids (≤ 10 mg of prednisone/day or equivalent), and/or NSAIDs during the trials).]
 | SIMPONI ± DMARDs | Placebo ± DMARDs
Patients treated | 1659 | 639
Adverse Reaction
Infections and infestations
Upper respiratory tract infection (nasopharyngitis, pharyngitis, laryngitis, and rhinitis) | 16% | 13%
Viral infections (such as influenza and herpes) | 5% | 3%
Bronchitis | 2% | 1%
Superficial fungal infections | 2% | 1%
Sinusitis | 2% | 1%
General disorders and administration site conditions
Injection site reaction (injection site erythema, urticaria, induration, pain, bruising, pruritus, irritation, paresthesia) | 6% | 2%
Investigations
Alanine aminotransferase increased | 4% | 3%
Aspartate aminotransferase increased | 3% | 2%
Vascular disorders
Hypertension | 3% | 2%
Nervous system disorders
Dizziness | 2% | 1%
Paresthesia | 2% | 1%
Gastrointestinal disorders
Constipation | 1% | <1%

Less Common Clinical Trial Adverse Drug Reactions

Adverse drug reactions that occurred <1% in adult SIMPONI-treated patients in the RA, PsA and AS clinical trials that do not appear in the Warnings and Precautions section included the following events listed by system organ class:

Infections and infestations:Septic shock, atypical mycobacterial infection, pyelonephritis, arthritis bacterial, bursitis infective

Neoplasms benign, malignant and unspecified:Leukemia

Skin and subcutaneous tissue disorders:Psoriasis (new onset or worsening, palmar/plantar and pustular), vasculitis (cutaneous)

Vascular disorders:Vasculitis (systemic)

Adults and Pediatric Patients Weighing at least 15 kg with Ulcerative Colitis

In general, adverse reactions reported in adult patients with UC in Trials UC-1, UC-2, and UC-3 were similar to those reported in clinical trials of patients with RA, PsA, and AS. Adverse reactions reported in the clinical trial of pediatric patients weighing at least 15 kg with UC were also similar to those reported in clinical trials of adults with UC and the other indicated populations. Additional adverse reactions reported in at least 10% of pediatric patients in the trial were headache (17%) and pyrexia (10%).

6.2 Postmarketing Experience

The following adverse reactions have been identified during post-approval use of golimumab. Because these reactions are reported voluntarily from a population of uncertain size, it is not always possible to reliably estimate their frequency or establish a causal relationship to SIMPONI exposure.

Immune system disorders:Serious systemic hypersensitivity reactions (including anaphylactic reaction) [see Warnings and Precautions (5.12)] , sarcoidosis

Neoplasms benign, malignant and unspecified:Melanoma, Merkel cell carcinoma [see Warnings and Precautions (5.2)]

Respiratory, thoracic and mediastinal disorders:Interstitial lung disease

Skin and subcutaneous tissue disorders: Skin exfoliation, lichenoid reactions, rash, bullous skin reactions

7 DRUG INTERACTIONS

7.1 Methotrexate

For the treatment of RA, SIMPONI should be used with methotrexate (MTX) [see Clinical Studies (14.1)] . Since the presence or absence of concomitant MTX did not appear to influence the efficacy or safety of SIMPONI in the treatment of PsA or AS, SIMPONI can be used with or without MTX in the treatment of PsA and AS [see Clinical Studies (14.2, 14.3) and Clinical Pharmacology (12.3)] .

7.2 Biological Products for RA, PsA, and/or AS

An increased risk of serious infections has been seen in clinical RA trials of other TNF blockers used in combination with anakinra or abatacept, with no added benefit; therefore, use of SIMPONI with abatacept or anakinra is not recommended [see Warnings and Precautions (5.7, 5.8)] . A higher rate of serious infections has also been observed in RA patients treated with rituximab who received subsequent treatment with a TNF blocker. The concomitant use of SIMPONI with biologics approved to treat RA, PsA, or AS is not recommended because of the possibility of an increased risk of infection.

7.3 Live Vaccines/Therapeutic Infectious Agents

Live vaccines should not be given concurrently with SIMPONI [see Warnings and Precautions (5.11)] .

Therapeutic infectious agents should not be given concurrently with SIMPONI [see Warnings and Precautions (5.11)] .

Infants born to women treated with SIMPONI during their pregnancy may be at increased risk of infection for up to 6 months. Administration of live vaccines to infants exposed to SIMPONI in uterois not recommended for 6 months following the mother's last SIMPONI injection during pregnancy [see Use in Specific Populations (8.1)] .

7.4 Cytochrome P450 Substrates

The formation of CYP450 enzymes may be suppressed by increased levels of cytokines (e.g., TNFα) during chronic inflammation. Therefore, it is expected that for a molecule that antagonizes cytokine activity, such as golimumab, the formation of CYP450 enzymes could be normalized. Upon initiation or discontinuation of SIMPONI in patients being treated with CYP450 substrates with a narrow therapeutic index, monitoring of the effect (e.g., warfarin) or drug concentration (e.g., cyclosporine or theophylline) is recommended and the individual dose of the drug product may be adjusted as needed.

8 USE IN SPECIFIC POPULATIONS

8.1 Pregnancy

Risk Summary

Available data from postmarketing case reports with golimumab use in pregnant women have not identified a drug-associated risk of major birth defects, miscarriage, or adverse maternal or fetal outcomes. An observational study of northern European births observed similar unadjusted rates of major birth defects in infants exposed in utero to golimumab compared to no treatment or non-biologic systemic therapy. However, this study had important limitations (see Data).

Monoclonal antibodies, such as golimumab, are transported across the placenta during the third trimester of pregnancy and may affect immune response in the in uteroexposed infant (see Clinical Considerations) . In an animal reproductive study, golimumab administered by the subcutaneous route to pregnant monkeys, during the period of organogenesis, at doses that produced exposures approximately 360 times the maximum recommended human dose (MRHD) had no adverse fetal effects (see Data) . In a pre- and post-natal development study with pregnant monkeys, subcutaneous administration of golimumab, during the later gestational and lactation periods, at doses producing maximal maternal blood concentrations approximately 460 times those found with the MRHD had no adverse developmental effects on infants (see Data). Data suggest that there are risks to the mother and the fetus associated with rheumatoid arthritis and ulcerative colitis in pregnancy (see Clinical Considerations).

All pregnancies have a background risk of birth defect, loss, or other adverse outcomes. The background risk of major birth defects and miscarriage for the indicated populations is unknown. In the U.S. general population, the estimated background risks of major birth defects and miscarriage in clinically recognized pregnancies is 2–4% and of miscarriage is 15–20%, respectively.

Clinical Considerations

Disease-associated Maternal and/or Embryo/Fetal Risk

Published data suggest that increased disease activity is associated with the risk of developing adverse pregnancy outcomes in women with rheumatoid arthritis or ulcerative colitis. Adverse pregnancy outcomes include preterm delivery (before 37 weeks gestation), low birth weight (less than 2500 g) infants, and small for gestational age at birth.

Fetal/Neonatal Adverse Reactions

Golimumab crosses the placenta during pregnancy. Another TNF-blocking monoclonal antibody administered during pregnancy was detected for up to 6 months in the serum of infants. Consequently, these infants may be at increased risk of infection. Administration of live vaccines to infants exposed to SIMPONI in utero is not recommended for 6 months following the mother's last SIMPONI injection during pregnancy [see Warnings and Precautions (5.11) and Drug Interactions (7.3)] .

Data

Human Data

An observational, exposure-based, cohort study based on data from the Swedish, Danish, and Finnish Medical Birth Registers conducted between 2006–2020 (Sweden and Denmark) and 2006–2019 (Finland) compared the risk of major birth defects in 134 live-born infants exposed to golimumab (116 from women treated for rheumatic conditions, 18 from women treated for ulcerative colitis) to no treatment or non-biologic systemic therapy. The unadjusted rate of major birth defects in infants exposed in uterowas similar across all groups. However, this study had important limitations such as a small number of pregnant women exposed to golimumab, a wide exposure ascertainment window, and incomplete risk adjustment for potential confounders.

Animal Data

In an embryofetal developmental toxicology study in which pregnant cynomolgus monkeys were treated with golimumab during the period organogenesis from gestation days (GD) 20 to 51, exposures up to 360 times greater than the exposure at the MRHD (on an area under the curve (AUC) basis with maternal subcutaneous doses up to 50 mg/kg twice weekly) produced no evidence of fetal malformations or embryotoxicity. There was no evidence of maternal toxicity. Umbilical cord blood samples collected at the end of the second trimester showed that fetuses were exposed to golimumab during gestation.

In a pre- and post-natal developmental study in which pregnant cynomolgus monkeys were treated with golimumab from gestation day 50 to postpartum day 33, maximal drug concentrations approximately 460 times greater than that found with the MRHD (on a maximum blood concentration (Cmax) basis at steady state with maternal subcutaneous doses up to 50 mg/kg twice weekly) were not associated with any evidence of developmental defects in infants. There was no evidence of maternal toxicity. Golimumab was present in fetal serum at the end of the second trimester and in neonatal serum from the time of birth and for up to 6 months postpartum.

8.2 Lactation

Risk Summary

There is no information regarding the presence of SIMPONI in human milk, the effects on breastfed infants, or the effects on milk production. Maternal IgG is known to be present in human milk. Golimumab is present in the milk of lactating cynomolgus monkeys (see Data) . If golimumab is transferred into human milk, the effects of local exposure in the gastrointestinal tract and potential limited systemic exposure in the infant to golimumab are unknown. The developmental and health benefits of breast-feeding should be considered along with the mother's clinical need for SIMPONI and any potential adverse effects on the breast-fed infants from SIMPONI, or from the underlying maternal condition.

Data

In the pre- and post-natal development study in cynomolgus monkeys in which golimumab was administered subcutaneously during pregnancy and lactation, golimumab was detected in the breast milk at concentrations that were approximately 400-fold lower than the maternal serum concentrations.

8.4 Pediatric Use

Ulcerative Colitis

The safety and effectiveness of SIMPONI for the treatment of moderately to severely active ulcerative colitis have been established in pediatric patients weighing at least 15 kg. Use of SIMPONI for this indication is supported by evidence from adequate and well-controlled studies in adults with additional safety and efficacy data from an open-label, study in 69 pediatric patients (4 to 17 years of age). The adverse reaction profile in these pediatric patients was similar to adults [see Adverse Reactions (6.1), Clinical Pharmacology (12.3), and Clinical Studies (14.5)]. Additionally, headache (17%) and pyrexia (10%) were reported in at least 10% of pediatric patients in the trial.

The safety and effectiveness of SIMPONI for the treatment of moderately to severely active ulcerative colitis have not been established in pediatric patients weighing less than 15 kg.

Polyarticular Juvenile Idiopathic Arthritis (pJIA)

The safety and efficacy of SIMPONI were evaluated in a multicenter, placebo-controlled, double-blind, randomized-withdrawal, parallel group study in 173 children (2 to 17 years of age) with active polyarticular juvenile idiopathic arthritis (pJIA) despite treatment with MTX for at least 3 months. Subjects were maintained on their stable dose of MTX at the same dose (mg/week) at study entry. Concurrent use of stable doses of oral corticosteroids (≤10 mg/day or 0.2 mg/kg/day prednisone or equivalent, whichever was less) and/or NSAIDs was permitted. In the 16 week open-label phase, all patients received MTX and SIMPONI 30 mg/m^2(maximum 50 mg) subcutaneously every 4 weeks. Patients who achieved an ACR Ped 30 response at Week 16 entered the randomized-withdrawal phase of the study and received MTX and either SIMPONI 30 mg/m^2(maximum 50 mg) or placebo every 4 weeks through Week 48.

The primary endpoint of the study was the proportion of patients who did not experience a flare between Week 16 and Week 48, among all subjects who entered the randomized withdrawal phase. The efficacy of SIMPONI in the treatment of pJIA was not demonstrated in this study because there was no statistical evidence of differences in flare rate between SIMPONI-treated patients and placebo patients between Weeks 16 and 48.

In this study, the frequency and type of the adverse reactions seen in children were generally similar to those observed in adults.

8.5 Geriatric Use

In the Phase 3 trials in RA, PsA, and AS, there were no overall differences in SAEs, serious infections, and AEs in SIMPONI-treated patients ages 65 or older (N=155) compared with younger SIMPONI-treated patients. Clinical studies of SIMPONI in patients with moderately to severely active ulcerative colitis did not include sufficient numbers of patients aged 65 and over to determine whether they respond differently than younger adult patients. Because there is a higher incidence of infections in the geriatric population in general, caution should be used in treating geriatric patients with SIMPONI [see Warnings and Precautions (5.1, 5.5)].

11 DESCRIPTION

Golimumab is a human IgG1κ monoclonal antibody specific for human tumor necrosis factor alpha (TNFα) that exhibits multiple glycoforms with molecular masses of approximately 150 to 151 kilodaltons. Golimumab was created using genetically engineered mice immunized with human TNF, resulting in an antibody with human-derived antibody variable and constant regions. Golimumab is produced by a recombinant cell line cultured by continuous perfusion and is purified by a series of steps that includes measures to inactivate and remove viruses.

SIMPONI ®(golimumab) Injection is a preservative-free, sterile, clear to slightly opalescent, colorless to light yellow solution of the golimumab antibody supplied in a single-dose prefilled syringe (with a passive needle safety guard) or a single-dose prefilled autoinjector.

Each 0.5 mL prefilled syringe and autoinjector contains 50 mg golimumab, L-histidine and L-histidine monohydrochloride monohydrate (0.44 mg), polysorbate 80 (0.08 mg), sorbitol (20.5 mg) and Water for Injection. Each 1 mL prefilled syringe and autoinjector contains 100 mg golimumab, L-histidine and L-histidine monohydrochloride monohydrate (0.87 mg), polysorbate 80 (0.15 mg), sorbitol (41.0 mg) and Water for Injection. The pH is approximately 5.5.

12 CLINICAL PHARMACOLOGY

12.1 Mechanism of Action

Golimumab is a human monoclonal antibody that binds to both the soluble and transmembrane bioactive forms of human TNFα. This interaction prevents the binding of TNFα to its receptors, thereby inhibiting the biological activity of TNFα (a cytokine protein). There was no evidence of the golimumab antibody binding to other TNF superfamily ligands; in particular, the golimumab antibody did not bind or neutralize human lymphotoxin. Golimumab did not lyse human monocytes expressing transmembrane TNF in the presence of complement or effector cells.

Elevated TNFα levels in the blood, synovium, and joints have been implicated in the pathophysiology of several chronic inflammatory diseases such as rheumatoid arthritis, psoriatic arthritis, and ankylosing spondylitis. TNFα is an important mediator of the articular inflammation that is characteristic of these diseases. The exact mechanism by which golimumab treats ulcerative colitis is unknown. Golimumab modulated the in vitro biological effects mediated by TNF in several bioassays, including the expression of adhesion proteins responsible for leukocyte infiltration (E-selectin, ICAM-1 and VCAM-1) and the secretion of proinflammatory cytokines (IL-6, IL-8, G-CSF and GM-CSF).

12.2 Pharmacodynamics

In clinical trials, decreases in C-reactive protein (CRP), interleukin (IL)-6, matrix metalloproteinase-3 (MMP-3), intercellular adhesion molecule (ICAM)-1 and vascular endothelial growth factor (VEGF) were observed following SIMPONI administration in patients with RA, PsA, and AS.

12.3 Pharmacokinetics

Absorption

Following subcutaneous administration of SIMPONI to healthy subjects and patients with active RA, the median time to reach maximum serum concentrations (Tmax) ranged from 2 to 6 days. A subcutaneous injection of 50 mg SIMPONI to healthy subjects produced a mean ± standard deviation maximum serum concentration (Cmax) of 3.2 ± 1.4 mcg/mL.

By cross-trial comparisons of mean AUCinfvalues following an IV or subcutaneous administration of SIMPONI, the absolute bioavailability of subcutaneous SIMPONI was estimated to be approximately 53%.

Distribution

Following a single IV administration over the dose range of 0.1 to 10.0 mg/kg in patients with active RA, mean volume of distribution ranged from 58 to 126 mL/kg. The volume of distribution for golimumab indicates that golimumab is distributed primarily in the circulatory system with limited extravascular distribution.

Metabolism

The exact metabolic pathway of golimumab is unknown.

Elimination

Following a single IV administration over the dose range of 0.1 to 10.0 mg/kg in patients with active RA, mean systemic clearance of SIMPONI was estimated to be 4.9 to 6.7 mL/day/kg.

Median terminal half-life values were estimated to be approximately 2 weeks in healthy subjects and patients with active RA, PsA or AS.

Population PK analyses indicated that concomitant use of NSAIDs, oral corticosteroids, or sulfasalazine did not influence the apparent clearance of golimumab.

Patients who developed anti-golimumab antibodies generally had lower steady-state serum trough concentrations of golimumab.

Dose Linearity

Golimumab exhibited dose-proportional pharmacokinetics (PK) in patients with active RA over the dose range of 0.1 to 10 mg/kg following a single intravenous (IV) dose. Following a single SC dose in healthy subjects, dose proportional pharmacokinetics were also observed over a dose range of 50 mg to 400 mg.

Single Dose Versus Multiple Doses

When 50 mg SIMPONI was administered subcutaneous to patients with RA, PsA, or AS every 4 weeks, serum concentrations appeared to reach steady state by Week 12. With concomitant use of methotrexate (MTX), treatment with 50 mg SIMPONI subcutaneous every 4 weeks resulted in a mean steady-state trough serum concentration of approximately 0.4–0.6 mcg/mL in patients with active RA, approximately 0.5 mcg/mL in patients with active PsA, and approximately 0.8 mcg/mL in patients with active AS. Patients with RA, PsA, and AS treated with SIMPONI 50 mg and MTX had approximately 52%, 36% and 21% higher mean steady-state trough concentrations of golimumab, respectively compared with those treated with SIMPONI 50 mg without MTX. The presence of MTX also decreased anti-golimumab antibody incidence from 7% to 2% [see Adverse Reactions (6.1)] . For RA, SIMPONI should be used with MTX. In the PsA and AS trials, the presence or absence of concomitant MTX did not appear to influence clinical efficacy and safety parameters [see Drug Interactions (7.1) and Clinical Studies (14.1)] .

When induction doses of 200 mg and 100 mg SIMPONI at week 0 and 2, respectively, followed by maintenance doses of 100 mg SIMPONI every 4 weeks were administered subcutaneously in patients with UC, serum golimumab concentrations reached steady-state by week 8 after the first maintenance dose. Treatment with 100 mg SIMPONI subcutaneous every 4 weeks during maintenance resulted in a mean steady-state trough serum concentration of approximately 1.8 ± 1.1 mcg/mL.

Effect of Weight on Pharmacokinetics in Adults

Higher apparent clearance of golimumab was associated with increasing weight. Treatment with the recommended maintenance dose regimen of SIMPONI 100 mg in adult patients with UC did not result in meaningful differences in clinical efficacy among different weight groups. Across the PsA and AS populations, no meaningful differences in clinical efficacy were observed among the subgroups by weight quartile. The RA trial in MTX-experienced and TNF-blocker-naïve patients (Trial RA-2) did show evidence of a reduction in clinical efficacy with increasing body weight, but this effect was observed for both tested doses of SIMPONI (50 mg and 100 mg). There is no need to adjust the dosage of SIMPONI in adult patients based on body weight.

Specific Populations

In adults, population PK analyses suggested no PK differences between male and female patients after body-weight adjustment in the RA, PsA and UC trials. In the AS trial, female patients showed 13% higher apparent clearance than male patients after body-weight adjustment. Subgroup analysis based on gender showed that both female and male patients achieved clinically significant response at the proposed clinical dose. Dosage adjustment based on gender is not needed.

Population PK analyses indicated that PK parameters of golimumab were not influenced by age in adult patients. Patients with age ≥ 65 years had apparent clearance of golimumab similar to patients with age < 65 years. No ethnicity-related PK differences were observed between Caucasians and Asians, and there were too few patients of other races to assess for PK differences.

No formal trial of the effect of renal or hepatic impairment on the PK of golimumab was conducted.

Pediatric Patients Weighing at Least 15 kg with Ulcerative Colitis

The pharmacokinetics of golimumab were studied in pediatric patients with UC aged 4 to 17 years. The pharmacokinetics of golimumab are predicted to be similar between adult patients and pediatric patients with UC. There are no expected clinically significant differences in golimumab systemic exposure between adult patients and pediatric patients weighing 15 kg and above who receive the recommended dosage [see Dosage and Administration (2.3)].

12.6 Immunogenicity

The observed incidence of anti-drug antibodies (ADA) is highly dependent on the sensitivity and specificity of the assay. Differences in assay methods preclude meaningful comparisons of the incidence of anti-drug antibodies in the studies described below with the incidence of anti-drug antibodies in other studies, including those of golimumab or of other golimumab products.

Results from the EIA Method

Using an enzyme immunoassay (EIA method), antibodies to golimumab were detected in 57 (4%) of SIMPONI-treated adult patients across the Phase 3 RA, PsA and AS trials through Week 24. Similar rates were observed in each of the 3 indications. Patients who received SIMPONI with concomitant MTX had a lower proportion of antibodies to golimumab than patients who received SIMPONI without MTX (approximately 2% vs. 7%, respectively).

With the EIA method, the presence of serum concentrations of golimumab can interfere with the detection of antibodies to golimumab leading to inconclusive results. In adult UC trials, 34 (3%), 341 (28%) and 823 (69%) of SIMPONI-treated patients were positive, negative and inconclusive for antibodies to golimumab, respectively. Treatment with concomitant immunomodulators (AZA, 6-MP or MTX) resulted in a lower proportion of patients with antibodies to golimumab than patients receiving SIMPONI without immunomodulators (2% vs. 4%, respectively).

Of the adult patients with a positive antibody response to golimumab in the Phase 2 and 3 trials, most were determined to have neutralizing antibodies to golimumab as measured by a cell-based functional assay.

Results from the Drug-Tolerant EIA Method

A drug-tolerant enzyme immunoassay (drug-tolerant EIA) method for detecting antibodies to golimumab was developed and validated, which eliminated the inconclusive category as reported above. This method is approximately 16-fold more sensitive than the original EIA method with less interference from golimumab in serum.

Based on the drug-tolerant EIA method, 246 (23%) of SIMPONI-treated patients across the Phase 3 RA, PsA and AS trials in adults, antibodies to golimumab were detected in 59 (16%), 106 (28%), and 81 (24%) patients, respectively. Treatment with concomitant MTX resulted in a lower proportion of patients with antibodies to golimumab than in patients receiving SIMPONI without MTX in RA patients (7% vs. 35%), in PsA patients (18% vs. 38%) and in AS patients (6% vs. 29%). A trend of decreasing drug concentrations with increasing antibody titers was observed. While an overall decrease in clinical efficacy for ADA positive patients compared with ADA negative patients was not observed in patients with RA (ACR 20: 75% vs. 75%), PsA (ACR 20: 72% vs. 66%) and AS (ASAS 20: 57% vs. 65%), higher titer antibodies may be associated with diminished efficacy.

In UC trials in adults, 254 (21%) of SIMPONI-treated patients were positive for antibodies to golimumab through week 54 while the remaining 941 (79%) patients were negative. Treatment with concomitant immunomodulators (AZA, 6-MP or MTX) in the UC trials resulted in a lower proportion of patients with antibodies to golimumab than in patients receiving SIMPONI without immunomodulators (12% vs. 26%). There is a trend of decreasing drug concentrations with increasing antibody titers. Although the development of antibodies to golimumab did not preclude clinical response, a trend toward decreased efficacy in ADA positive patients was observed compared to ADA negative patients in the UC trials (clinical response 38% vs. 53%).

In the pediatric UC trial, 22% (15/69) of SIMPONI-treated patients developed ADA to golimumab through the final safety visit using the drug-tolerant EIA method. Of the 15 subjects who tested positive for ADA, 20% (3/15) tested positive for neutralizing antibodies. The incidence of antibodies to golimumab was comparable between pediatric and adult patients with UC. Pediatric UC patients who developed antibodies to golimumab generally had lower trough steady-state serum concentrations of golimumab. While there is insufficient data to assess whether the observed ADA-associated pharmacokinetic changes reduce effectiveness, a trend toward decreased efficacy in ADA positive patients was observed compared to ADA negative patients in the pediatric UC trial.

13 NONCLINICAL TOXICOLOGY

13.1 Carcinogenesis, Mutagenesis, Impairment of Fertility

Long-term animal studies of golimumab have not been conducted to evaluate its carcinogenic potential. Mutagenicity studies have not been conducted with golimumab. A fertility study conducted in mice using an analogous anti-mouse TNFα antibody administered by the intravenous route at doses up to 40 mg/kg once per week showed no impairment of fertility.

14 CLINICAL STUDIES

14.1 Rheumatoid Arthritis

The efficacy and safety of SIMPONI were evaluated in 3 multicenter, randomized, double-blind, controlled trials (Trials RA-1, RA-2, and RA-3) in 1542 patients ≥ 18 years of age with moderately to severely active RA, diagnosed according to the American College of Rheumatology (ACR) criteria, for at least 3 months prior to administration of trial agent. Patients were required to have at least 4 swollen and 4 tender joints. SIMPONI was administered subcutaneously at doses of 50 mg or 100 mg every 4 weeks. Double-blinded controlled efficacy data were collected and analyzed through Week 24. Patients were allowed to continue stable doses of concomitant low dose corticosteroids (equivalent to ≤ 10 mg of prednisone a day) and/or NSAIDs and patients may have received oral MTX during the trials.

Trial RA-1 evaluated 445 patients who were previously treated (at least 8 to 12 weeks prior to administration of trial agent) with one or more doses of a biologic TNF blocker without a serious adverse reaction. Patients may have discontinued the biologic TNF blocker for a variety of reasons. Patients were randomized to receive placebo (N=150), SIMPONI 50 mg (N=147), or SIMPONI 100 mg (N=148). Patients were allowed to continue stable doses of concomitant MTX, sulfasalazine (SSZ), and/or hydroxychloroquine (HCQ) during the trial. The use of other DMARDs including cytotoxic agents or other biologics was prohibited.

Trial RA-2 evaluated 444 patients who had active RA despite a stable dose of at least 15 mg/week of MTX and who had not been previously treated with a biologic TNF blocker. Patients were randomized to receive background MTX (N=133), SIMPONI 50 mg + background MTX (N=89), SIMPONI 100 mg + background MTX (N=89), or SIMPONI 100 mg monotherapy (N=133). The use of other DMARDs including SSZ, HCQ, cytotoxic agents, or other biologics was prohibited.

Trial RA-3 evaluated 637 patients with active RA who were MTX naïve and had not previously been treated with a biologic TNF blocker. Patients were randomized to receive MTX (N=160), SIMPONI 50 mg + MTX (N=159), SIMPONI 100 mg + MTX (N=159), or SIMPONI 100 mg monotherapy (N=159). For patients receiving MTX, MTX was administered at a dose of 10 mg/week beginning at Week 0 and increased to 20 mg/week by Week 8. The use of other DMARDs including SSZ, HCQ, cytotoxic agents, or other biologics was prohibited.

The primary endpoint in Trial RA-1 and Trial RA-2 was the percentage of patients achieving an ACR 20 response at Week 14 and the primary endpoint in Trial RA-3 was the percentage of patients achieving an ACR 50 response at Week 24.

In Trials RA-1, RA-2, and RA-3, the median duration of RA disease was 9.4, 5.7, and 1.2 years and 99%, 75%, and 54% of the patients used at least one DMARD in the past, respectively. Approximately 77% and 57% of patients received concomitant NSAIDs and low dose corticosteroids, respectively, in the 3 pooled RA trials.

Clinical Response

In the 3 RA trials, a greater percentage of patients treated with the combination of SIMPONI and MTX achieved ACR responses at Week 14 (Trials RA-1 and RA-2) and Week 24 (Studies RA-1, RA-2, and RA-3) versus patients treated with the MTX alone. There was no clear evidence of improved ACR response with the higher SIMPONI dose group (100 mg) compared to the lower SIMPONI dose group (50 mg). In Trials RA-2 and RA-3, the SIMPONI monotherapy groups were not statistically different from the MTX monotherapy groups in ACR responses. Table 3 shows the proportion of patients with the ACR response for the SIMPONI 50 mg and control groups in Trials RA-1, RA-2, and RA-3. In the subset of patients who received SIMPONI in combination with MTX in Trial RA-1, the proportion of patients achieving ACR 20, 50 and 70 responses at Week 14 were 40%, 18%, and 12%, respectively, in the SIMPONI 50 mg + MTX group (N=101) compared with 17%, 6%, and 2%, respectively, in the placebo + MTX group (N=103). Table 4 shows the percent improvement in the components of the ACR response criteria for the SIMPONI 50 mg + MTX and MTX groups in Trial RA-2. The percentage of patients achieving ACR 20 responses by visit for Trial RA-2 is shown in Figure 1. ACR 20 responses were observed in 38% of patients in the SIMPONI 50 mg + MTX group at the first assessment (Week 4) after the initial SIMPONI administration.

Table 3: Trials RA-1, RA-2, and RA-3 Proportion of Patients with an ACR Response [Approximately 78% and 58% of the patients received concomitant NSAIDs and low dose corticosteroids (equivalent to ≤ 10 mg of prednisone a day), respectively, during the 3 pooled RA trials.]
 | Trial RA-1 Active RA previously treated with one or more doses of TNF blockers |  | Trial RA-2 Active RA, despite MTX |  | Trial RA-3 Active RA, MTX Naïve
 | Placebo ± DMARDs [DMARDs in Trial RA-1 included MTX, HCQ, and/or SSZ (about 68%, 8%, and 5% of patients received MTX, HCQ, and SSZ, respectively).] | SIMPONI 50 mg ± DMARDs | Background MTX | SIMPONI 50 mg + Background MTX | MTX | SIMPONI 50 mg + MTX
N [N reflects randomized patients.] | 150 | 147 | 133 | 89 | 160 | 159
ACR 20
Week 14 | 18% | 35% | 33% | 55% | NA [NA = Not applicable, as data was not collected at Week 14 in Trial RA-3.] | NA
Week 24 | 16% | 31% | 28% | 60% | 49% | 62%
ACR 50
Week 14 | 7% | 15% | 10% | 35% | NA | NA
Week 24 | 4% | 16% | 14% | 37% | 29% | 40%
ACR 70
Week 14 | 2% | 10% | 4% | 13% | NA | NA
Week 24 | 2% | 9% | 5% | 20% | 16% | 24% [Not significantly different from MTX monotherapy.]

Table 4: Trial RA-2 ─ Median Percent Improvement from Baseline in the Individual ACR Components at Week 14 [In Trial RA-2, about 70% and 85% of patients received concomitant low dose corticosteroids (equivalent to ≤ 10 mg of prednisone a day) and/or NSAIDs during the trials, respectively.]
 | Background MTX | SIMPONI 50 mg + Background MTX
N [N reflects randomized patients; actual number of patients evaluable for each endpoint may vary.] | 133 | 89
Number of swollen joints (0–66)
Baseline | 12 | 13
Week 14 | 38% | 62%
Number of tender joints (0–68)
Baseline | 21 | 26
Week 14 | 30% | 60%
Patient's assessment of pain (0–10)
Baseline | 5.7 | 6.1
Week 14 | 18% | 55%
Patient's global assessment of disease activity (0–10)
Baseline | 5.3 | 6.0
Week 14 | 15% | 45%
Physician's global assessment of disease activity (0–10)
Baseline | 5.7 | 6.1
Week 14 | 35% | 55%
HAQ score (0–3)
Baseline | 1.25 | 1.38
Week 14 | 10% | 29%
CRP (mg/dL)
Baseline | 0.8 | 1.0
Week 14 | 2% | 44%
Note: Baseline values are medians.

Figure 1: Trial RA-2 – Percentage of Patients Achieving ACR 20 Response by Visit: Randomized Patients [The same patients may not have responded at each timepoint.]

Physical Function Response in Patients with RA

In Trials RA-1 and RA-2, the SIMPONI 50 mg groups demonstrated a greater improvement compared to the control groups in the change in mean Health Assessment Questionnaire Disability Index (HAQ-DI) score from baseline to Week 24: 0.23 vs. 0.03 in RA-1, 0.47 vs. 0.13 in RA-2, respectively. Also in Trials RA-1 and RA-2, the SIMPONI 50 mg groups compared to the control groups had a greater proportion of HAQ responders (change from baseline > 0.22) at Week 24: 43% vs. 27%, 65% vs. 35%, respectively.

14.2 Psoriatic Arthritis

The safety and efficacy of SIMPONI were evaluated in a multicenter, randomized, double-blind, placebo-controlled trial in 405 adult patients with moderately to severely active PsA (≥ 3 swollen joints and ≥ 3 tender joints) despite NSAID or DMARD therapy (Trial PsA). Patients in this trial had a diagnosis of PsA for at least 6 months with a qualifying psoriatic skin lesion of at least 2 cm in diameter. Previous treatment with a biologic TNF blocker was not allowed. Patients were randomly assigned to placebo (N=113), SIMPONI 50 mg (N=146), or SIMPONI 100 mg (N=146) given subcutaneously every 4 weeks. Patients were allowed to receive stable doses of concomitant MTX (≤ 25 mg/week), low dose oral corticosteroids (equivalent to ≤ 10 mg of prednisone a day), and/or NSAIDs during the trial. The use of other DMARDs including SSZ, HCQ, cytotoxic agents, or other biologics was prohibited. The primary endpoint was the percentage of patients achieving ACR 20 response at Week 14. Placebo-controlled efficacy data were collected and analyzed through Week 24.

Patients with each subtype of PsA were enrolled, including polyarticular arthritis with no rheumatoid nodules (43%), asymmetric peripheral arthritis (30%), distal interphalangeal (DIP) joint arthritis (15%), spondylitis with peripheral arthritis (11%), and arthritis mutilans (1%). The median duration of PsA disease was 5.1 years, 78% of patients received at least one DMARD in the past, and approximately 48% of patients received MTX, and 16% received low dose oral steroids.

Clinical Response in Patients with PsA

SIMPONI ± MTX, compared with placebo ± MTX, resulted in significant improvement in signs and symptoms as demonstrated by the proportion of patients with an ACR 20 response at Week 14 in Trial PsA (see Table 5). There was no clear evidence of improved ACR response with the higher SIMPONI dose group (100 mg) compared to the lower SIMPONI dose group (50 mg). ACR responses observed in the SIMPONI-treated groups were similar in patients receiving and not receiving concomitant MTX. Similar ACR 20 responses at Week 14 were observed in patients with different PsA subtypes. However, the number of patients with arthritis mutilans was too small to allow meaningful assessment. SIMPONI 50 mg treatment also resulted in significantly greater improvement compared with placebo for each ACR component in Trial PsA (Table 6). Treatment with SIMPONI resulted in improvement in enthesitis and skin manifestations in patients with PsA. However, the safety and efficacy of SIMPONI in the treatment of patients with plaque psoriasis has not been established.

The percentage of patients achieving ACR 20 responses by visit for Trial PsA is shown in Figure 2. ACR 20 responses were observed in 31% of patients in the SIMPONI 50 mg + MTX group at the first assessment (Week 4) after the initial SIMPONI administration.

Table 5: Trial PsA - Proportion of Patients with ACR Responses
 | Placebo ± MTX [In Trial PsA, about 48%, 16%, and 72% of the patients received stable doses of MTX (≤ 25 mg/week), low dose corticosteroids (equivalent to ≤ 10 mg of prednisone a day), and NSAIDs, respectively.] | SIMPONI 50 mg ± MTX
N [N reflects randomized patients.] | 113 | 146
ACR 20
Week 14 | 9% | 51%
Week 24 | 12% | 52%
ACR 50
Week 14 | 2% | 30%
Week 24 | 4% | 32%
ACR 70
Week 14 | 1% | 12%
Week 24 | 1% | 19%
Bold text indicates primary endpoint.

Table 6: Trial PsA - Percent Improvement in ACR Components at Week 14
 | Placebo ± MTX [In Trial PsA, about 48%, 16%, and 78% of the patients received stable doses of MTX (≤ 25 mg/week), low dose corticosteroids (equivalent to ≤ 10 mg of prednisone a day), and NSAIDs, respectively.] | SIMPONI 50 mg ± MTX
N [N reflects randomized patients; actual number of patients evaluable for each endpoint may vary by timepoint.] | 113 | 146
Number of swollen joints (0–66)
Baseline | 10.0 | 11.0
Week 14 | 8% | 60%
Number of tender joints (0–68)
Baseline | 18.0 | 19.0
Week 14 | 0% | 54%
Patient's assessment of pain (0–10)
Baseline | 5.4 | 5.8
Week 14 | -1% | 48%
Patient's global assessment of disease activity (0–10)
Baseline | 5.2 | 5.2
Week 14 | 2% | 49%
Physician's global assessment of disease activity (0–10)
Baseline | 5.2 | 5.4
Week 14 | 7% | 59%
HAQ score (0–10)
Baseline | 1.0 | 1.0
Week 14 | 0% | 28%
CRP (mg/dL) (0–10)
Baseline | 0.6 | 0.6
Week 14 | 0% | 40%
Note: Baseline are median values.

Figure 2: Trial PsA – Percentage of ACR 20 PsA Responders by Visit: Randomized Patients [The same patients may not have responded at each timepoint.]

Physical Function Response in Patients with PsA

In Trial PsA, SIMPONI 50 mg demonstrated a greater improvement compared to placebo in the change in mean Health Assessment Questionnaire Disability Index (HAQ-DI) score from baseline to Week 24 (0.33 and -0.01, respectively). In addition, the SIMPONI 50 mg group compared to the placebo group had a greater proportion of HAQ responders (≥ 0.3 change from baseline) at Week 24: 43% vs. 22%, respectively.

14.3 Ankylosing Spondylitis

The safety and efficacy of SIMPONI were evaluated in a multicenter, randomized, double-blind, placebo-controlled trial in 356 adult patients with active ankylosing spondylitis according to modified New York criteria for at least 3 months (Trial AS). Patients had symptoms of active disease [defined as a Bath AS Disease Activity Index (BASDAI) ≥ 4 and VAS for total back pain of ≥ 4, on scales of 0 to 10 cm] despite current or previous NSAID therapy. Patients were excluded if they were previously treated with a biologic TNF blocker or if they had complete ankylosis of the spine. Patients were randomly assigned to placebo (N=78), SIMPONI 50 mg (N=138), or SIMPONI 100 mg (N=140) administered subcutaneously every 4 weeks. Patients were allowed to continue stable doses of concomitant MTX, sulfasalazine (SSZ), hydroxychloroquine (HCQ), low dose corticosteroids (equivalent to < 10 mg of prednisone a day), and/or NSAIDs during the trial. The use of other DMARDs including cytotoxic agents or other biologics was prohibited.

The primary endpoint was the percentage of patients achieving an Assessment in Ankylosing Spondylitis (ASAS) 20 response at Week 14. Placebo-controlled efficacy data were collected and analyzed through Week 24.

In Trial AS, the median duration of AS disease was 5.6 years, median duration of inflammatory back pain was 12 years, 83% were HLA-B27 positive, 24% had prior joint surgery or procedure, and 55% received at least one DMARD in the past. During the trial, the use of concomitant DMARDs and/or NSAIDs was as follows: MTX (20%), SSZ (26%), HCQ (1%), low dose oral steroids (16%), and NSAIDs (90%).

Clinical Response in Patients with AS

In Trial AS, SIMPONI ± DMARDs treatment, compared with placebo ± DMARDs, resulted in a significant improvement in signs and symptoms as demonstrated by the proportion of patients with an ASAS 20 response at Week 14 (see Table 7). There was no clear evidence of improved ASAS response with the higher SIMPONI dose group (100 mg) compared to the lower SIMPONI dose group (50 mg). Table 8 shows the percent improvement in the components of the ASAS response criteria for the SIMPONI 50 mg ± DMARDs and placebo ± DMARDs groups in Trial AS.

The percentage of patients achieving ASAS 20 responses by visit for Trial AS is shown in Figure 3. ASAS 20 responses were observed in 48% of patients in the SIMPONI 50 mg + MTX group at the first assessment (Week 4) after the initial SIMPONI administration.

Table 7: Trial AS – Proportion of ASAS Responders at Weeks 14 and 24
 | Placebo ± DMARDs [During the trial, the concomitant use of stable doses of DMARDs was as follows: MTX (21%), SSZ (25%), and HCQ (1%). About 16% and 89% of patients received stable doses of low dose oral steroids and NSAIDs during the trial, respectively.] | SIMPONI 50 mg ± DMARDs
N [N reflects randomized patients.] | 78 | 138
Responders, % of patients
ASAS 20
Week 14 | 22% | 59%
Week 24 | 23% | 56%
ASAS 40
Week 14 | 15% | 45%
Week 24 | 15% | 44%
Bold text indicates primary endpoint.

Table 8: Trial AS ─ Median Percent Improvement in ASAS Components at Week 14
 | Placebo ± DMARDs [During the trial, the concomitant use of stable doses of DMARDs was as follows: MTX (21%), SSZ (25%), and HCQ (1%). About 16% and 89% of patients received stable doses of low dose oral steroids and NSAIDs during the trial, respectively.] | SIMPONI 50 mg ± DMARDs
N [N reflects randomized patients.] | 78 | 138
ASAS components
Patient global assessment (0–10)
Baseline | 7.2 | 7.0
Week 14 | 13% | 47%
Total back pain (0–10)
Baseline | 7.6 | 7.5
Week 14 | 9% | 50%
BASFI (0–10) [BASFI is Bath Ankylosing Spondylitis Functional Index.]
Baseline | 4.9 | 5.0
Week 14 | -3% | 37%
Inflammation (0–10) [Inflammation is the mean of 2 patient-reported stiffness self-assessments in the Bath AS Disease Activity Index (BASDAI).]
Baseline | 7.1 | 7.1
Week 14 | 6% | 59%

Figure 3: Trial AS – Percentage of AS Patients Achieving ASAS 20 Response by Visit: Randomized Patients [The same patients may not have responded at each timepoint.]

14.4 Adult Ulcerative Colitis

The efficacy and safety of SIMPONI was evaluated in 2 multicenter, randomized, double-blind, placebo-controlled clinical trials in adults with moderately to severely active ulcerative colitis (UC). Trial UC-1 (NCT00487539) was a 6-week induction trial. Trial UC-2 (NCT00488631) was a randomized-withdrawal maintenance trial that evaluated 456 patients who achieved clinical response with SIMPONI induction and tolerated SIMPONI treatment.

In Trial UC-1 moderately to severely active UC was, defined as a Mayo score of 6 to 12 [the Mayo score ranges from 0 to 12 and has 4 subscales that are each scored from 0 (normal) to 3 (most severe): stool frequency, rectal bleeding, findings on endoscopy, and physician global assessment]. At baseline, subjects also had an endoscopy subscore of 2 or 3 on a 3-point scale (an endoscopy score of 2 is defined by marked erythema, absent vascular pattern, friability, erosions; and a score of 3 is defined by spontaneous bleeding, ulceration). Patients were corticosteroid dependent (i.e., an inability to successfully taper corticosteroids without a return of the symptoms of UC) or had an inadequate response to or had failed to tolerate at least one of the following therapies: oral aminosalicylates, oral corticosteroids, azathioprine, or 6-mercaptopurine.

Trial UC-1 was divided into 2 parts. In Part 1 (dose finding), patients were randomized to one of 4 treatment groups: 400 mg SIMPONI administered subcutaneously (SC) at Week 0 and 200 mg at Week 2 (400/200 mg), 200 mg SIMPONI SC at Week 0 and 100 mg at Week 2 (200/100 mg), 100 mg SIMPONI SC at Week 0 and 50 mg at Week 2 (100/50 mg), or placebo SC at Weeks 0 and 2. In Part 2 (dose confirming), efficacy was evaluated in 761 patients who were randomized to receive either 400 mg SIMPONI SC at Week 0 and 200 mg at Week 2, 200 mg SIMPONI SC at Week 0 and 100 mg at Week 2, or placebo SC at Weeks 0 and 2. SIMPONI 100/50-mg SC was not evaluated in Part 2; its safety and effectiveness has not been established in UC. Concomitant stable doses of oral aminosalicylates (5-ASA), oral corticosteroids (less than 40 mg/day), azathioprine (AZA), 6-mercaptopurine (6-MP), and/or methotrexate (MTX) were permitted. Patients who received previous TNF inhibitors were excluded. The primary endpoint in UC-1 was the percent of patients in clinical response at Week 6, defined as a decrease from baseline in the Mayo score by ≥ 30% and ≥ 3 points, accompanied by a decrease in the rectal bleeding subscore of ≥ 1 or a rectal bleeding subscore of 0 (no blood seen) or 1 (streaks of blood with stool less than half the time).

Trial UC-2 evaluated 456 patients who achieved clinical response with SIMPONI induction and tolerated SIMPONI treatment. Patients were randomized to receive SIMPONI 50 mg, SIMPONI 100 mg or placebo administered subcutaneously every 4 weeks. Concomitant stable doses of oral aminosalicylates, azathioprine, 6-mercaptopurine, and/or methotrexate were permitted. Corticosteroids were to be tapered at the start of the maintenance trial. The primary endpoint in UC-2 was the percent of patients maintaining clinical response through Week 54.

Clinical Response, Clinical Remission and Improvement of Endoscopic Appearance of the Mucosa

In Trial UC-1, a greater proportion of patients achieved clinical response, clinical remission and had improvement of endoscopic appearance of the mucosa at Week 6 in the SIMPONI 200/100 mg group compared with the placebo group. The SIMPONI 400/200 mg group did not demonstrate additional clinical benefit over the SIMPONI 200/100 mg group. Clinical response was defined as a decrease from baseline in the Mayo score of ≥ 30% and ≥ 3 points, accompanied by a decrease in the rectal bleeding subscore of ≥ 1 or a rectal bleeding subscore of 0 or 1. Clinical remission was defined as a Mayo score ≤ 2 points, with no individual subscore > 1. Improvement of endoscopic appearance of the mucosa was defined as a Mayo endoscopy subscore of 0 (normal or inactive disease) or 1 (erythema, decreased vascular pattern, mild friability).

In Trial UC-2, a greater proportion of patients maintained clinical response through Week 54 in the SIMPONI 100 mg group compared with the placebo group. In Trial UC-2, SIMPONI-treated patients in clinical response (which included the subset of patients in clinical remission) in Trial UC-1, were again assessed for clinical remission at Week 30 and Week 54. A greater proportion of patients had clinical remission at both Weeks 30 and 54 without demonstrating a loss of response at any time point through Week 54 in the SIMPONI 100 mg group compared with the placebo group.

These results are shown in Table 9 below.

Table 9: The Proportion of Patients with UC in Clinical Response, Clinical Remission and with Improvement of Endoscopic Appearance of the Mucosa in Trials UC-1 and UC-2
Trial UC-1 (6-Week Induction Trial)
 | Placebo N=251 | SIMPONI 200/100 mg N=253 | Treatment difference (95% CI)
Clinical response [Patients who had a prohibited change in concomitant UC medication, an ostomy or colectomy, discontinued trial agent due to lack of therapeutic effect, or a dose adjustment in Trial UC-2 were considered not to be in clinical response, clinical remission or have an improvement in endoscopic appearance of the mucosa from the time of the event onward.] at Week 6 | 30% | 51% | 21% (12%, 29%) [p<0.0001;]
Clinical remission at Week 6 | 6% | 18% | 11% (6%, 17%)
Improvement of endoscopic appearance of the mucosa at Week 6 | 29% | 42% | 14% (5%, 22%) [p=0.0014;]
Trial UC-2 (54-Week Maintenance Trial) [Results in Trial UC-2 are based on patients who were in clinical response to SIMPONI at trial entry.]
 | Placebo N=154 | SIMPONI 100 mg N=151 | Treatment difference (95% CI)
Clinical response through Week 54 [Patients were assessed for UC disease activity by partial Mayo score every 4 weeks (loss of response was confirmed by endoscopy). Therefore, a patient who maintained clinical response was in response at each evaluation through Week 54.] | 31% | 50% | 19% (8%, 29%) [p<0.001;]
Clinical remission at both Week 30 and Week 54 [A patient had to be in remission at both Weeks 30 and 54 (without demonstrating a loss of response at any time point through Week 54) to achieve sustained remission.] | 16% | 28% | 12% (3%, 21%) [p=0.004]

14.5 Pediatric Ulcerative Colitis

The efficacy and safety of SIMPONI was evaluated in a multi-center, open-label pediatric study of 69 patients (NCT03596645). Efficacy was assessed in 66 patients weighing at least 15 kg with moderately to severely active ulcerative colitis defined as a Mayo score of 6 to 12 with an endoscopy subscore of ≥2 who had an inadequate response to corticosteroids, 6‑mercaptopurine (6‑MP), or azathioprine (AZA), or who were intolerant to or had medical contraindications for such therapies. Patients with prior exposure to TNF blockers were ineligible. Of the 66 subjects assessed for efficacy, the mean age was 13.4 years (range 4 to 17 years), the median weight was 51 kg, and 53% were female. Twenty-four percent identified as Hispanic or Latino; 71% identified as White, 18% as Asian, 3% as American Indian or Alaskan Native, 3% as Black, and 2% identified as part of multiple racial subgroups.

Patients weighing 15 to less than 45 kg received SIMPONI subcutaneously at 120 mg/m^2 at dosages of 120 mg/m^2 at Week 0, 60 mg/m^2 at Week 2 and 60 mg/m^2 every 4 weeks from Week 6 onward.

Patients weighing at least 45 kg received SIMPONI 200 mg at Week 0, 100 mg at Week 2 and 100 mg every 4 weeks from Week 6 onward.

The recommended body-weight tiered dosage for pediatric patients weighing 15 to less than 40 kg and 40 to less than 45 kg differs from the body surface area-based dosage administered in this study. There are no anticipated clinically relevant differences in efficacy between the recommended and studied pediatric dosages of SIMPONI [see Dosage and Administration (2.3) and Clinical Pharmacology (12.3)].

At weeks 6, and 54, efficacy was assessed by the Mayo score.

Efficacy Endpoints Week 6

The results of the primary endpoint of clinical remission at Week 6 and secondary endpoint of clinical response at Week 6, both assessed by Mayo score are shown in Table 10.

Table 10: Proportion of Pediatric Patients Weighing at Least 15 kg with UC in Clinical Remission and Clinical Response at Week 6
Endpoint | SIMPONI n (%) [90% CI] N=66
Clinical remission at Week 6 [Clinical remission is defined as a Mayo score ≤2 points, with no individual subscore >1.] | 21 (32%) [22%, 41%]
Clinical response at Week 6 [Clinical response is defined as a decrease from baseline in the Mayo score by ≥ 30% and ≥ 3 points, with either a decrease from baseline in the rectal bleeding subscore of ≥ 1 or a rectal bleeding subscore of 0 or 1.] | 38 (58%) [48%, 68%]

Additional Secondary Endpoints

Of the 38 pediatric subjects with clinical response at Week 6, 13 subjects (34%) were in clinical remission and 15 subjects (39%) had endoscopic improvement, defined as an endoscopy subscore of 0 or 1 based on local endoscopy, at Week 54. Of the 21 subjects in clinical remission at Week 6, 12 subjects (57%) maintained clinical remission at Week 54.

16 HOW SUPPLIED/STORAGE AND HANDLING

SIMPONI ®(golimumab) Injection is a preservative-free, sterile, clear to slightly opalescent, colorless to light yellow solution for subcutaneous use in a single-dose prefilled autoinjector (contains a prefilled glass syringe) or a single-dose prefilled glass syringe. The Type 1 glass syringe has a coated stopper. The fixed stainless-steel needle (5 bevel, 27G, ½ inch) is covered with a needle shield to prevent leakage of the solution through the needle and to protect the needle during handling prior to subcutaneous administration. The needle shield is made of a dry natural rubber containing latex.

50 mg/0.5 mL single-dose prefilled syringe | 1 pack | NDC 57894-070-01
100 mg/mL single-dose prefilled syringe | 1 pack | NDC 57894-071-01
50 mg/0.5 mL single-dose prefilled SmartJect® autoinjector | 1 pack | NDC 57894-070-02
100 mg/mL single-dose prefilled SmartJect® autoinjector | 1 pack | NDC 57894-071-02

Storage and Handling

Refrigerate SIMPONI between 36 °F to 46 °F (2 °C to 8 °C) in the original carton to protect from light until the time of use. Do not freeze. Do not shake. Do not use SIMPONI beyond the expiration date (EXP) on the carton or the expiration date on the prefilled syringe (observed through the viewing window) or the prefilled SmartJect® autoinjector.

If needed, SIMPONI may be stored at room temperature up to 77 °F (25 °C) for a maximum single period of 30 days in the original carton to protect from light. Once a syringe or autoinjector has been stored at room temperature, do not return the product to the refrigerator. If not used within 30 days at room temperature, discard SIMPONI.

17 PATIENT COUNSELING INFORMATION

See FDA-approved patient labeling (Medication Guide and Instructions for Use)

Patients should be advised of the potential benefits and risks of SIMPONI. Physicians should instruct their patients to read the Medication Guide before starting SIMPONI therapy and to read it each time the prescription is renewed.

Infections

Inform patients that SIMPONI may lower the ability of their immune system to fight infections. Advise patients not to start taking SIMPONI if they have an active infection. Instruct patients to contact their healthcare provider if they develop any symptoms of infection, including tuberculosis, invasive fungal infections, and hepatitis B reactivation [see Warnings and Precautions (5.1, 5.5)].

Malignancies

Inform patients that SIMPONI may increase their risk of lymphoma and other malignancies while receiving SIMPONI [see Warnings and Precautions (5.2)].

Hypersensitivity Reactions

Advise patients to stop taking SIMPONI and contact their healthcare provider immediately if they experience any symptoms of hypersensitivity reactions while taking SIMPONI [see Warnings and Precautions (5.12)].

Advise latex-sensitive patients that the needle cover on the prefilled syringe as well as the prefilled syringe in the prefilled SmartJect® autoinjector contains dry natural rubber (a derivative of latex) [see How Supplied/Storage and Handling (16)].

Other Medical Conditions

Advise patients to report any signs of new or worsening medical conditions such as congestive heart failure, demyelinating disorders, autoimmune diseases, liver disease, or cytopenias [see Warnings and Precautions (5.3, 5.4, 5.5, 5.6, 5.10)].

Instructions for Safe Administration

The first injection should be performed under the supervision of a qualified healthcare professional. Only the prefilled syringe is recommended for pediatric self-injection.

SIMPONI Prefilled Syringe

- Adult and pediatric patients 12 years of age and older may self-inject with SIMPONI prefilled syringe.

SIMPONI SmartJect® Autoinjector

- Adult patients may self-inject with SIMPONI SmartJect® autoinjector.
- Use of the SmartJect® autoinjector for pediatric self-administration has not been evaluated.

If a patient or caregiver is to administer SIMPONI, he/she should be instructed in injection techniques and their ability to inject subcutaneously should be assessed to ensure the proper administration of SIMPONI.

Advise the patient to read the FDA-approved Instructions for Use and provide the following instructions to patients:

- Prior to use, remove the prefilled syringe or the prefilled SmartJect® autoinjector from the refrigerator and allow SIMPONI to sit at room temperature outside of the carton for at least 30 minutes and out of the reach of children.
- Do not warm SIMPONI in any other way. For example, do not warm SIMPONI in a microwave or in hot water.
- Do not remove the prefilled syringe needle cover or SmartJect® autoinjector cap while allowing SIMPONI to reach room temperature. Remove these immediately before injection.
- Do not pull the autoinjector away from the skin until you hear a first "click" sound and then a second "click" sound (the injection is finished and the needle is pulled back). It usually takes about 3 to 6 seconds but may take up to 15 seconds for you to hear the second "click" after the first "click". If the autoinjector is pulled away from the skin before the injection is completed, a full dose of SIMPONI may not be administered.
- A puncture-resistant container for disposal of needles and syringes should be used. Patients or caregivers should be instructed in the technique of proper syringe and needle disposal, and be advised not to reuse these items.

Manufactured by:
Janssen Biotech, Inc.
Horsham, PA 19044, USA
U.S. License No. 1864
For patent information: www.janssenpatents.com
© Johnson & Johnson and its affiliates 2025

MEDICATION GUIDE
SIMPONI® (SIM-po-nee)
(golimumab)
injection, for subcutaneous use

What is the most important information I should know about SIMPONI?
SIMPONI is a medicine that affects your immune system. SIMPONI can lower the ability of your immune system to fight infections. Some people have serious infections while taking SIMPONI, including tuberculosis (TB), and infections caused by bacteria, fungi, or viruses that spread throughout their body. Some people have died from these serious infections.

- Your doctor should test you for TB and hepatitis B before starting SIMPONI.
- Your doctor should monitor you closely for signs and symptoms of TB during treatment with SIMPONI.

You should not start taking SIMPONI if you have any kind of infection unless your doctor says it is okay.

Before starting SIMPONI, tell your doctor if you:

- think you have an infection or have symptoms of an infection such as:

- fever, sweat, or chills
- muscle aches
- cough
- shortness of breath
- blood in phlegm
- weight loss

- warm, red, or painful skin or sores on your body
- diarrhea or stomach pain
- burning when you urinate or urinate more often than normal
- feel very tired

- are being treated for an infection.
- get a lot of infections or have infections that keep coming back.
- have diabetes, HIV, or a weak immune system. People with these conditions have a higher chance for infections.
- have TB, or have been in close contact with someone with TB.
- live, have lived, or traveled to certain parts of the country (such as the Ohio and Mississippi River valleys and the Southwest) where there is an increased chance for getting certain kinds of fungal infections (histoplasmosis, coccidioidomycosis, blastomycosis). These infections may happen or become more severe if you use SIMPONI. Ask your doctor if you do not know if you have lived in an area where these infections are common.
- have or have had hepatitis B.
- use the medicine ORENCIA (abatacept), KINERET (anakinra), ACTEMRA (tocilizumab) or RITUXAN (rituximab).

After starting SIMPONI, call your doctor right away if you have any symptoms of an infection. SIMPONI can make you more likely to get infections or make worse any infection that you have.
Cancer

- For children and adults taking TNF-blocker medicines, including SIMPONI, the chances of getting cancer may increase.
- There have been cases of unusual cancers in children and teenage patients taking TNF-blocking agents.
- People with inflammatory diseases including rheumatoid arthritis, psoriatic arthritis, or ankylosing spondylitis, especially those with very active disease, may be more likely to get lymphoma.
- Some people receiving medicines that are like SIMPONI, called TNF blockers, developed a rare type of cancer called hepatosplenic T cell lymphoma. This type of cancer often results in death. Most of these people were male teenagers or young men. Also, most people were being treated for Crohn's disease or ulcerative colitis with a TNF blocker and another medicine called azathioprine or 6 mercaptopurine (6-MP).
- Some people treated with SIMPONI have developed certain kinds of skin cancer. If any changes in the appearance of your skin or growths on your skin occur during or after your treatment with SIMPONI, tell your doctor.
- You should see your doctor periodically for skin examinations, especially if you have a history of skin cancer.

What is SIMPONI?
SIMPONI is a prescription medicine called a Tumor Necrosis Factor (TNF) blocker. SIMPONI is used to treat:

- adults with the medicine methotrexate to treat moderately to severely active rheumatoid arthritis (RA)
- adults with active psoriatic arthritis (PsA) alone or with methotrexate
- adults with active ankylosing spondylitis (AS)
- adults and children weighing at least 33 pounds (15 kg) with moderately to severely active ulcerative colitis (UC)

You may continue to use other medicines that help treat your condition while taking SIMPONI, such as non-steroidal anti-inflammatory drugs (NSAIDs) and prescription steroids, as recommended by your doctor.

It is not known if SIMPONI is safe and effective in children under 18 years of age in RA, PsA, and AS or weighing less than 33 pounds (15 kg) in pediatric ulcerative colitis.

What should I tell my doctor before starting treatment with SIMPONI?
SIMPONI may not be right for you. See " What is the most important information I should know about SIMPONI?" Before starting SIMPONI, tell your doctor about all your medical conditions, including if you:

- have an infection.
- have or have had lymphoma or any other type of cancer.
- have or had heart failure.
- have or have had a condition that affects your nervous system, such as multiple sclerosis or Guillain-Barré syndrome.
- have recently received or are scheduled to receive a vaccine. People taking SIMPONI should not receive live vaccines or treatment with a weakened bacteria (such as BCG for bladder cancer). People taking SIMPONI can receive non-live vaccines.
- have a baby and you were using SIMPONI during your pregnancy. Tell your baby's doctor before your baby receives any vaccine. Your baby may have an increased chance of getting an infection for up to 6 months after birth.
- are allergic to rubber or latex. The needle cover on the prefilled syringe and SmartJect® autoinjector contains dry natural rubber.
- are pregnant or planning to become pregnant. It is not known if SIMPONI will harm your unborn baby.
- are breastfeeding or plan to breastfeed. You and your doctor should decide if you will take SIMPONI or breastfeed.

Tell your doctor about all the medicines you take, including prescription and over-the-counter medicines, vitamins, and herbal supplements.
Especially, tell your doctor if you:

- use ORENCIA (abatacept) or KINERET (anakinra). You should not take SIMPONI while you are also taking ORENCIA (abatacept) or KINERET (anakinra).
- use other TNF blocker medicines, including REMICADE (infliximab), HUMIRA (adalimumab), ENBREL (etanercept), or CIMZIA (certolizumab pegol).
- receive RITUXAN (rituximab) or ACTEMRA (tocilizumab).

Ask your doctor if you are not sure if your medicine is one listed above.
Keep a list of all your medicine with you to show your doctor and pharmacist each time you get a new medicine.

How should I use SIMPONI?

- SIMPONI is given as an injection under the skin (subcutaneous injection).
- SIMPONI comes in a prefilled syringe or SmartJect® autoinjector. Your doctor will prescribe the type that is best for you.
- If your doctor decides that you, your child, or a caregiver may be able to give your injections of SIMPONI at home, you should receive training on the right way to prepare and inject SIMPONI. Do not try to inject SIMPONI yourself until you have been shown the right way to give the injections by your doctor or nurse.
  - Adults and children 12 years of age and older may self-inject with SIMPONI prefilled syringe.
  - Only adults may self-inject with SIMPONI SmartJect® autoinjector.
- Use SIMPONI exactly as prescribed by your doctor. Your doctor will tell you how much SIMPONI to inject and when to inject it depending on your medical condition.
- See the detailed Instructions for Usethat comes with your SIMPONI for information about the right way to prepare and give your SIMPONI injections at home.
- Do not miss any doses of SIMPONI. If you miss a dose of SIMPONI, inject the missed dose as soon as possible. Then, take your next dose at your regular scheduled time. In case you are not sure when to inject SIMPONI, call your doctor or pharmacist.

What are the possible side effects of SIMPONI?
SIMPONI can cause serious side effects, including:
See " What is the most important information I should know about SIMPONI?"
Serious Infections.

- Some patients have an increased chance of getting serious infections while receiving SIMPONI. These serious infections include TB and infections caused by viruses, fungi, or bacteria that have spread throughout the body. Some patients die from these infections. Do not start using SIMPONI if you have an active infection. If you get an infection while receiving treatment with SIMPONI your doctor will treat your infection and may need to stop your SIMPONI treatment. Tell your doctor right away if you have any of the following signs of an infection while taking or after taking SIMPONI:

- a fever
- feel very tired
- have a cough

- have flu-like symptoms
- warm, red, or painful skin

- Your doctor will examine you for TB and perform a test to see if you have TB. If your doctor feels that you are at risk for TB, you may be treated with medicine for TB before you begin treatment with SIMPONI and during treatment with SIMPONI. Even if your TB test is negative your doctor should carefully monitor you for TB infections while you are taking SIMPONI. People who had a negative TB skin test before receiving SIMPONI have developed active TB. Tell your doctor if you have any of the following symptoms while taking or after taking SIMPONI:

- cough that does not go away
- low grade fever

- weight loss
- loss of body fat and muscle (wasting)

Hepatitis B infection in people who carry the virus in their blood.

- If you are a carrier of the hepatitis B virus (a virus that affects the liver), the virus can become active while you use SIMPONI. Your doctor should do blood tests before you start treatment with SIMPONI and while you are using SIMPONI. Tell your doctor if you have any of the following symptoms of a possible hepatitis B infection:

- feel very tired
- dark urine
- skin or eyes look yellow
- little or no appetite
- vomiting
- muscle aches

- clay-colored bowel movements
- fevers
- chills
- stomach discomfort
- skin rash

Heart failure, including new heart failure or worsening of heart failure that you already have, can happen in people who use TNF-blocker medicines including SIMPONI.If you develop new or worsening heart failure with SIMPONI, you may need to be treated in a hospital, and it may result in death.

- If you have heart failure before starting SIMPONI, your condition should be watched closely during treatment with SIMPONI.
- Call your doctor right away if you get new or worsening symptoms of heart failure during treatment with SIMPONI (such as shortness of breath or swelling of your lower legs or feet, or sudden weight gain).

Nervous System Problems.Rarely, people using TNF-blocker medicines, including SIMPONI, have nervous system problems such as multiple sclerosis or Guillain-Barré syndrome. Tell your doctor right away if you get any of these symptoms:

- vision changes
- weakness in your arms or legs

- numbness or tingling in any part of your body

Immune System Problems.Rarely, people using TNF-blocker medicines have developed symptoms that are like the symptoms of Lupus. Tell your doctor if you have any of these symptoms:

- a rash on your cheeks or other parts of the body
- sensitivity to the sun
- new joint or muscle pains

- becoming very tired
- chest pain or shortness of breath
- swelling of the feet, ankles, or legs

Liver Problems.Liver problems can happen in people who use TNF-blocker medicines, including SIMPONI. These problems can lead to liver failure and death. Call your doctor right away if you have any of these symptoms:

- feel very tired
- skin or eyes look yellow

- poor appetite or vomiting
- pain on the right side of your stomach (abdomen)

Blood Problems.Low blood counts have been seen with SIMPONI. Your body may not make enough blood cells that help fight infections or help stop bleeding. Symptoms include fever, bruising or bleeding easily, or looking pale. Your doctor will check your blood counts before and during treatment with SIMPONI.

Allergic Reactions.Allergic reactions can happen in people who use TNF-blocker medicines, including SIMPONI. Some reactions may be serious and can be life-threatening. Some of these reactions can happen after receiving your first dose of SIMPONI. Stop using SIMPONI and call your doctor right away if you have any of these symptoms of an allergic reaction:

- hives
- swollen face

- breathing trouble
- chest pain

The most common side effects of SIMPONI include:

- upper respiratory infection (runny nose, sore throat, and hoarseness or laryngitis)
- reaction at the site of injection (redness, swelling, itching, pain, bruising, or tingling)
- viral infections such as flu and oral cold sores

Psoriasis. Some people using SIMPONI had new psoriasis or worsening of psoriasis they already had. Tell your doctor if you develop red scaly patches or raised bumps that are filled with pus. Your doctor may decide to stop your treatment with SIMPONI.

These are not all of the possible side effects of SIMPONI. Tell your doctor about any side effect that bothers you or does not go away. Call your doctor for medical advice about side effects. You may report side effects to FDA at 1-800-FDA-1088.

How should I store SIMPONI?

- Refrigerate SIMPONI between 36 °F to 46 °F (2 °C to 8 °C).
- If needed, you may store SIMPONI at room temperature up to 77 °F (25 °C) for one period of time up to 30 days.
  - Write the date of that you remove SIMPONI from the refrigerator on the carton.
  - If SIMPONI has reached room temperature, do not put it back in the refrigerator.
  - Throw away SIMPONI if it has been kept at room temperature for 30 days and has not been used.
- Do not freeze SIMPONI.
- Keep SIMPONI in the original carton to protect it from light when not being used.
- Do not shake SIMPONI.
- Do not use SIMPONI after the expiration date on the carton or on the prefilled syringe or SmartJect ®autoinjector.

Keep SIMPONI and all medicines out of the reach of children.

General information about the safe and effective use of SIMPONI.

Medicines are sometimes prescribed for purposes other than those listed in a Medication Guide. Do not use SIMPONI for a condition for which it was not prescribed. Do not give SIMPONI to other people, even if they have the same symptoms that you have. It may harm them.

This Medication Guide summarizes the most important information about SIMPONI. If you would like more information, talk to your doctor. You can ask your doctor or pharmacist for information about SIMPONI that is written for health professionals. For more information go to www.simponi.com or call 1-800-JANSSEN (1-800-526-7736).

What are the ingredients in SIMPONI?

Active ingredient: golimumab.

Inactive ingredients: L-histidine, and L-histidine monohydrochloride monohydrate, polysorbate 80, sorbitol, and water for injection. SIMPONI does not contain preservatives.

Manufactured by: Janssen Biotech, Inc. Horsham, PA 19044, USA. U.S. License No. 1864.
For patent information: www.janssenpatents.com
© Johnson & Johnson and its affiliates 2025

This Medication Guide has been approved by the U.S. Food and Drug Administration.

Revised: Oct 2025

INSTRUCTIONS FOR USE

SIMPONI®(SIM-po-nee)
(golimumab)
injection, for subcutaneous use

This Instructions for Use contains information on how to inject SIMPONI using the SmartJect Autoinjector.

Please read this Instructions for Use before using SIMPONI SmartJect and each time you get a refill. There may be new information. This leaflet does not take the place of talking with your doctor about your medical condition or your treatment.

Important information

If your doctor decides that you or a caregiver may be able to give your SIMPONI injections at home, you should receive training on the right way to prepare and inject SIMPONI using SmartJect.

Do not try to inject SIMPONI yourself until you have been shown the right way to give the injections by your doctor or nurse.

Do not pinch the skin while injecting. Pinching the skin can cause failure of the device and injury, including needlestick injury.

Do not inject into the arm to avoid failure of the device or injury.

Store SIMPONI in the refrigerator at 36°F to 46°F(2°C to 8°C).

Do not freeze SmartJect.

Do not shake SmartJect.

If needed, store SIMPONI at room temperature, up to 77°F (25°C) for one period of time up to 30 days. Do not return it to the refrigerator. Throw away (dispose of) if not used within 30 days at room temperature.

Keep SIMPONI in the original carton to protect from light before use.

Keep SIMPONI and all medicines out of the reach of children.

Your SmartJect at-a-glance

1. Preparing to inject SIMPONI using Smartject

Take out SmartJect

Take SmartJect out of the refrigerator and remove it from the carton. Place on a flat surface out of reach of children.

SmartJect should sit at room temperature for at least 30 minutes to ensure proper injection.

Do not warm any other way.

Do not remove the cap yet.

Inspect SmartJect

Check the expiration date ('EXP') on the back of SmartJect.

Do not use SIMPONI SmartJect if the expiration date has passed. Call your doctor or pharmacist for a refill.

Check the security seal on the cap.

Do not inject if the seal is broken.

Gather supplies

While SmartJect sits at room temperature for 30 minutes, gather your supplies:

- 1 Alcohol swab
- 1 Cotton ball or gauze pad
- 1 Sharps container (See Step 3)

Check liquid in the SmartJect

After 30 minutes, check the liquid in the viewing window. It should be clear to slightly yellow and may contain tiny white or clear particles.

It is also normal to see a small air bubble.

Do not inject if the liquid is cloudy or discolored, or has large particles.

Do not inject into the arm to avoid failure of the device or injury.

Choose injection site

Select from the following areas for your injection:

- Front of thighs
- Lower abdomen (do not use the 2-inch area around your navel (belly-button)
- Do not inject into the arms

Choose a different site within your preferred area for each injection.

Do not inject into skin that is tender, bruised, red, scaly or hard. Avoid areas with scars or stretch marks.

Wash hands and clean injection site

Wash your hands well with soap and warm water.

Wipe your chosen injection site with an alcohol swab and allow it to dry.

Do not touch, fan or blow on the injection site after you have cleaned it.

2. Injecting SIMPONI using SmartJect

Remove cap

Twist the cap to break the security seal, then pull it straight off. Dispose of the cap right away.

It is important to inject within 5 minutes of removing the cap.

Do not put the cap back on, this may damage the hidden needle.

Do not inject if SmartJect is dropped without the cap on.

Do not pinch the skin while injecting. Pinching the skin can cause failure of the device and injury, including needlestick injury.

Position

Hold SmartJect comfortably with one hand above the blue button and position it straight onto your skin, as shown.

Make sure the green safety sleeve is stable and as flat as possible against your skin. If the device is not stable during the injection, you risk bending the needle.

Do not pinch your skin while positioning SmartJect onto your skin.

Do not pinch the skin to avoid injury, including needlestick injury.

Push down

Push the open end of SmartJect against your skin at a 90-degree angle. Apply enough pressure to slide the green safety sleeve up and to keep it inside the clear cover. Only the wider part of the green safety sleeve stays outside of the clear cover.

Do not touch or press the blue button while pushing SmartJect against your skin.

The green safety sleeve helps prevent accidental injections.

Pushing the blue button before the safety sleeve is pressed down can lead to device failure.

Inject without pinching the skin.

Press button and wait

Keep holding SmartJect against your skin. Use your other hand to press the raised part of the blue button to start your injection. Do not press the button until SmartJect is pressed against your skin and the safety sleeve slides into the clear cover.

You will hear a loud 1st 'click' as you press the button. This is normal, the medication is just beginning to be delivered. You may or may not feel a needle prick.

Listen for 2nd 'click'

Keep holding SmartJect against your skin until you hear the 2nd 'click' (or for 15 seconds). It usually takes about 3-6 seconds, but may take up to 15 seconds for you to hear the second 'click' sound.

The 2nd 'click' means the injection is complete and you can lift SmartJect from your skin.

Check the viewing window

After lifting SmartJect from your skin, look for the yellow indicator in the viewing window to confirm SmartJect worked properly. The yellow indicator will fill about half of the viewing window.

If you do not see the yellow indicator, call 800-JANSSEN (800-526-7736).

Do not administer a second dose without speaking to your doctor.

3. Disposing of SIMPONI SmartJect

Dispose of your SmartJect

Put your used SmartJect in an FDA-cleared sharps disposal container right away after use.

Do not recycle your used sharps disposal container.

For more information, see " Helpful tips".

Check injection site

There may be a small amount of blood or liquid at the injection site.

Hold pressure over your skin with a cotton ball or gauze pad until any bleeding stops.

Do not rub the injection site.

If needed, cover injection site with a bandage. Your injection is now complete!

Need help?

Call your doctor or pharmacist to talk about any questions you may have. For additional assistance or to share your feedback call 800-JANSSEN (800-526-7736).

Helpful tips
If you are having difficulty injecting:

✓ Make sure the cap is removed.
✓ Make sure SmartJect is pushed against your skin, so the green safety sleeve slides into the clear cover.
✓ Make sure you are pressing the raised part of button.
✓ If the button is hard to depress, do not press the button harder. Let go of the button, then lift SmartJect and start again. Ensure no pressure is on the button until the green safety sleeve is fully depressed against the skin, then press the button.
✓ Try a different injection site.

Additional Disposal Information

If you do not have an FDA-cleared sharps disposal container, you may use a household container that is:

- made of a heavy-duty plastic
- can be closed with a tight-fitting, puncture-resistant lid, without sharps being able to come out
- upright and stable during use
- leak-resistant
- properly labeled to warn of hazardous waste inside the container

When your sharps disposal container is almost full, you will need to follow your community guidelines for the right way to dispose of your sharps disposal container. There may be state or local laws about how you should throw away used needles and syringes.

For more information about safe sharps disposal, and for specific information about sharps disposal in the state that you live in, go to the FDA's website at: www.fda.gov/safesharpsdisposal

This Instructions for Use has been approved by the U.S. Food and Drug Administration.

Manufactured by:
Janssen Biotech, Inc.
Horsham, PA 19044, USA
US License No. 1864

Revised: September 2025

Instructions for Use
SIMPONI®
(SIM-po-nee)
(golimumab)
Prefilled Syringe

Important

SIMPONI comes as a single-dose prefilled syringe containing one 50 mg or one 100 mg dose. Each SIMPONI prefilled syringe can only be used one time. Throw away (dispose of) the used prefilled syringe (See Step 3) after one dose, even if there is medicine left in it. Do not reuse your SIMPONI prefilled syringe.

The SIMPONI prefilled syringe should be administered by a healthcare provider, adult, child 12 years of age and older, or caregiver.

If your healthcare provider decides that you, your child or a caregiver may be able to give your injections of SIMPONI at home, you should receive training on the right way to prepare and inject SIMPONI using the prefilled syringe before attempting to inject. Do not try to inject yourself until you have been shown the right way to give the injections by your healthcare provider.

Read this Instructions for Use before using your SIMPONI prefilled syringe and each time you get a refill. There may be new information. This leaflet does not take the place of talking with your healthcare provider about your medical condition or your treatment.

The SIMPONI prefilled syringe is intended for injection under the skin, not into the muscle or vein. After injection, the needle will retract into the body of the device and lock into place.

Storage information

Store SIMPONI in the refrigerator between 36 °F to 46 °F (2 °C to 8 °C).

If needed, store SIMPONI at room temperature, up to 77 °F (25 °C) for one period of time up to 30 days. Do not return it to the refrigerator. Throw away (dispose of) if not used within 30 days at room temperature.

Do notfreeze SIMPONI prefilled syringe.

Do notshake SIMPONI prefilled syringe.

Keep SIMPONI prefilled syringe in the original carton to protect from light before use.

Keep SIMPONI prefilled syringe and all medicines out of the reach of children.

Prefilled syringe parts

Before use

After use

You will need these supplies:

- 1 SIMPONI prefilled syringe

Not provided in the SIMPONI prefilled syringe carton:

- 1 Alcohol swab
- 1 Cotton ball or gauze pad
- 1 Adhesive bandage
- 1 Sharps container(See Step 3)

Inspect carton

Remove your SIMPONI prefilled syringe carton from the refrigerator.

Remove the prefilled syringe from the carton and let it sit on a flat surface at room temperature for at least 30 minutes before use.

Do not warm the prefilled syringe any other way.

Check the expiration date ('EXP') on the back panel of the carton and on the prefilled syringe (through the viewing window).

Do not use your prefilled syringe if the expiration date has passed.

Do not inject SIMPONI if the perforations on the carton are broken. Call your healthcare provider or pharmacist for a refill.

Choose injection site

Select from the following areas for your injection:

- Front of thighs (recommended)
- Lower stomach area (lower abdomen), except for a 2-inch area right around your navel (belly-button)
- Back of upper arms (only if someone else is giving you the injection)

Choose a different site within your preferred area for each injection.

Do not inject into skin that is tender, bruised, red, hard, thick or scaly.

Do not inject into areas with scars or stretch marks.

Clean injection site

Wash your hands well with soap and warm water.

Wipe your chosen injection site with an alcohol swab and allow it to dry.

Do not touch, fan, or blow on the injection site after you have cleaned it.

Inspect liquid

Check the SIMPONI prefilled syringe liquid in the viewing window. It should be clear and colorless to light yellow and may contain tiny white or clear particles. You may also see one or more air bubbles. This is normal.

Do not inject if the liquid is cloudy or discolored, or has large particles. Call your healthcare provider or pharmacist for a refill.

Remove needle cover

Hold your prefilled syringe by the body and pull needle cover straight off. It is normal to see a drop of liquid.

Inject SIMPONI within 5 minutes of removing the needle cover.

Do not put needle cover back on, as this may damage the needle or cause a needle stick injury.

Do not touch needle or let it touch any surface.

Do not use a SIMPONI prefilled syringe if it is dropped. Call your healthcare provider or pharmacist for a refill.

Position fingers and insert needle

Place your thumb, index and middle fingers directly under the finger flange, as shown.

Do not touch plunger or area above finger flange as this may cause the needle safety device to activate.

Use your other hand to pinch skin at the injection site. Position syringe at about a 45 degree angle to the skin.

It is important to pinch enough skin to inject under the skin and not into the muscle.

Insert needle with a quick, dart-like motion.

Release pinch and reposition hand

Use your free hand to grasp the body of the prefilled syringe.

Press plunger

Place thumb from the opposite hand on the plunger and press the plunger all the way down until it stops.

Release pressure from plunger

The safety guard will cover the needle and lock into place, removing the needle from your skin.

Dispose of your prefilled syringe

Put your used SIMPONI prefilled syringe in an approved sharps disposal container right away after use.

Do not throw away (dispose of) your used SIMPONI prefilled syringe in your household trash.

Do not recycle your used sharps disposal container.

For more information, see "How should I dispose of the used prefilled syringe?"

Check injection site

There may be a small amount of blood or liquid at the injection site. Hold pressure over your skin with a cotton ball or gauze pad until any bleeding stops.

Do not rub the injection site.

If needed, cover injection site with a bandage.

Need help?

Call your healthcare provider to talk about any questions you may have. For additional assistance or to share your feedback call 1-800-JANSSEN (1-800-526-7736).

How should I dispose of the used prefilled syringe?

If you do not have an approved sharps disposal container, you may use a household container that is:

- made of a heavy-duty plastic
- can be closed with a tight-fitting, puncture-resistant lid, without sharps being able to come out
- upright and stable during use
- leak-resistant
- properly labeled to warn of hazardous waste inside the container

When your sharps disposal container is almost full, you will need to follow your community guidelines for the right way to dispose of your sharps disposal container. There may be state or local laws about how you should throw away (dispose of) used needles and syringes.

For more information about safe sharps disposal, and for specific information about sharps disposal in the state that you live in, go to the FDA's website at: www.fda.gov/safesharpsdisposal

This Instructions for Use has been approved by the U.S. Food and Drug Administration.

Revised: October 2025

Manufactured by:
Janssen Biotech, Inc.
Horsham, PA 19044, USA
US License No. 1864

For patent information: www.janssenpatents.com
© Johnson & Johnson and its affiliates 2025

PRINCIPAL DISPLAY PANEL - 50 mg/0.5 mL Syringe Carton

NDC 57894-070-01

FOR SUBCUTANEOUS INJECTION

Sterile solution in a single dose
prefilled syringe. Discard unused portion.

See package insert for dosing information.

No U.S. standard of potency.

This Product Contains
Dry Natural Rubber.

Rx only.

Simponi®
golimumab

50 mg / 0.5 mL

One single-dose prefilled syringe

PRINCIPAL DISPLAY PANEL - 50 mg/0.5 mL Autoinjector Syringe Carton

NDC 57894-070-02

FOR SUBCUTANEOUS INJECTION

Sterile solution in a single-dose
SmartJect®autoinjector.

Discard unused portion.

See package insert for dosing information.

No U.S. standard of potency.

This Product Contains
Dry Natural Rubber.

Rx only.

Simponi®
golimumab

50 mg / 0.5 mL

One single-dose SmartJect®autoinjector

PRINCIPAL DISPLAY PANEL - 100 mg/mL Syringe Carton

NDC 57894-071-01

FOR SUBCUTANEOUS INJECTION

Sterile solution in a single-dose
prefilled syringe. Discard unused portion.

See package insert for dosing information.

No U.S. standard of potency.

This Product Contains
Dry Natural Rubber.

Rx only.

Simponi®
golimumab

100 mg/mL

One single-dose prefilled syringe

PRINCIPAL DISPLAY PANEL - 100 mg/mL Autoinjector Syringe Carton

NDC 57894-071-02

FOR SUBCUTANEOUS INJECTION

Sterile solution in a single-dose
SmartJect®autoinjector.

Discard unused portion.

See package insert for dosing information.

No U.S. standard of potency.

This Product Contains
Dry Natural Rubber.

Rx only.

Simponi®
golimumab

100 mg/mL

One single-dose SmartJect®autoinjector